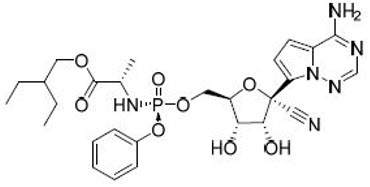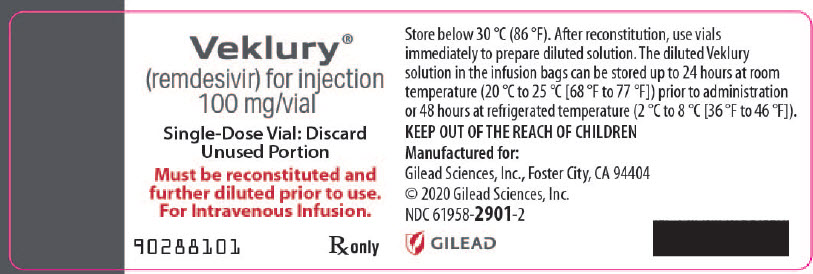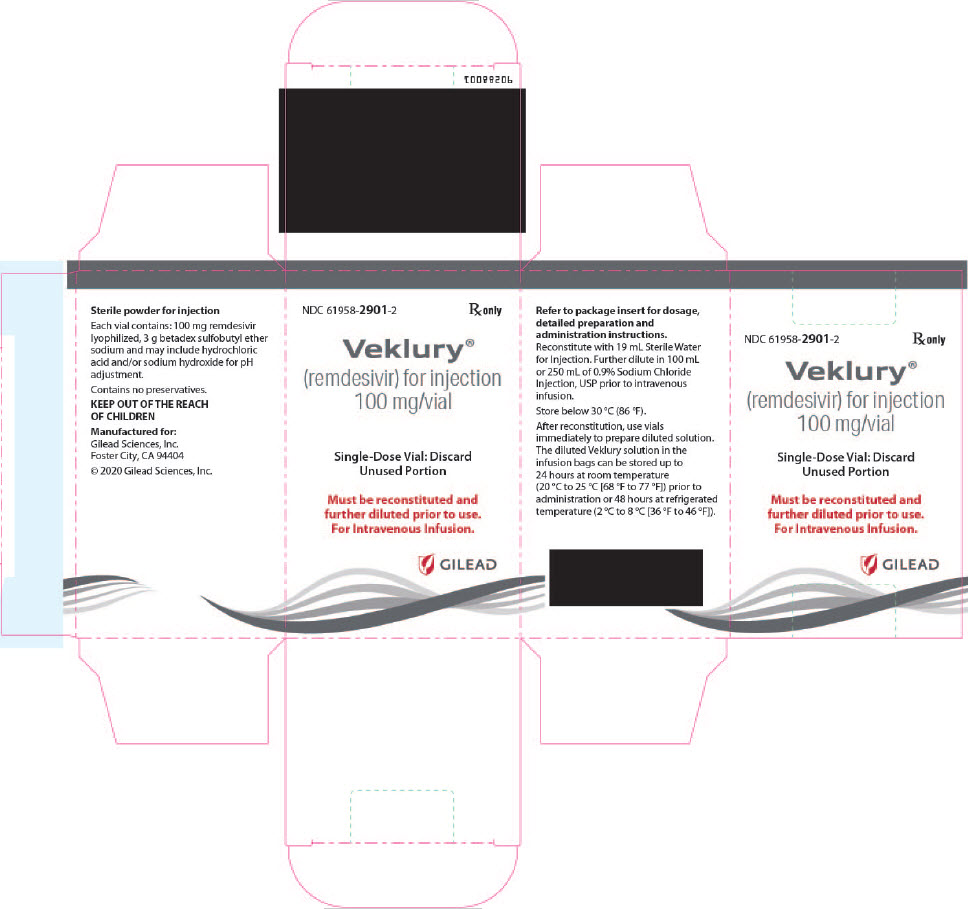 DRUG LABEL: Veklury
NDC: 61958-2902 | Form: INJECTION
Manufacturer: Gilead Sciences, Inc.
Category: prescription | Type: HUMAN PRESCRIPTION DRUG LABEL
Date: 20260212

ACTIVE INGREDIENTS: REMDESIVIR 5 mg/1 mL
INACTIVE INGREDIENTS: BETADEX SULFOBUTYL ETHER SODIUM; WATER; HYDROCHLORIC ACID; SODIUM HYDROXIDE

HIGHLIGHTS OF PRESCRIBING INFORMATION

These highlights do not include all the information needed to use VEKLURY safely and effectively. See full prescribing information for VEKLURY.
VEKLURY® (remdesivir) for injection, for intravenous use
Initial U.S. Approval: 2020

RECENT MAJOR CHANGES

Dosage and Administration
Dosage and Administration Overview (2.1) | 10/2025
Dosage Preparation and Administration (2.5) | 10/2025
Storage of Prepared Dosages (2.6) | 10/2025

1 INDICATIONS AND USAGE

VEKLURY is a severe acute respiratory syndrome coronavirus 2 (SARS-CoV-2) nucleotide analog RNA polymerase inhibitor indicated for the treatment of coronavirus disease 2019 (COVID-19) in adults and pediatric patients (birth to less than 18 years of age weighing at least 1.5 kg) who are:

- Hospitalized, or
- Not hospitalized and have mild-to-moderate COVID-19, and are at high risk for progression to severe COVID-19, including hospitalization or death. (1)

2 DOSAGE AND ADMINISTRATION

- Testing: In all patients, before starting VEKLURY and during treatment as clinically appropriate, perform hepatic laboratory testing. Assess prothrombin time before starting VEKLURY and monitor as clinically appropriate. (2.2)
- Recommended dosage:
  - Adults and pediatric patients weighing at least 40 kg: a single loading dose of VEKLURY 200 mg on Day 1 followed by once-daily maintenance doses of VEKLURY 100 mg from Day 2 via intravenous infusion. (2.3)
  - Pediatric patients (birth to less than 18 years of age) weighing 1.5 kg to less than 40 kg: Recommended dosage is based on weight. Refer to Table 1 of the full prescribing information for specific dosing guidelines based on body weight. (2.3)
- Hospitalized patients: The treatment course of VEKLURY should be initiated as soon as possible after diagnosis of symptomatic COVID-19 has been made. (2.3)
  - For hospitalized patients requiring invasive mechanical ventilation and/or ECMO, the recommended total treatment duration is 10 days. (2.3)
  - For hospitalized patients not requiring invasive mechanical ventilation and/or ECMO, the recommended treatment duration is 5 days. If a patient does not demonstrate clinical improvement, treatment may be extended for up to 5 additional days for a total treatment duration of up to 10 days. (2.3)
- Non-hospitalized patients: The treatment course of VEKLURY should be initiated as soon as possible after diagnosis of symptomatic COVID-19 has been made and within 7 days of symptom onset. (2.3)
  - For non-hospitalized patients diagnosed with mild-to-moderate COVID-19 who are at high risk for progression to severe COVID-19, including hospitalization or death, the recommended total treatment duration is 3 days (2.3).
- Renal impairment: No dosage adjustment of VEKLURY is recommended in patients with any degree of renal impairment, including those on dialysis. (2.4)
- Administer VEKLURY via intravenous (IV) infusion over 30 to 120 minutes. (2.5)
- Dose preparation and administration: Refer to the full prescribing information for further details. (2.5)
- Storage of prepared dosages: VEKLURY contains no preservative. (2.6)

3 DOSAGE FORMS AND STRENGTHS

For injection: 100 mg of remdesivir as a lyophilized powder, in a single-dose vial. (3)

4 CONTRAINDICATIONS

VEKLURY is contraindicated in patients with a history of clinically significant hypersensitivity reactions to VEKLURY or any components of the product. (4)

5 WARNINGS AND PRECAUTIONS

- Hypersensitivity including infusion-related and anaphylactic reactions: Hypersensitivity reactions have been observed during and following administration of VEKLURY. Slower infusion rates, with a maximum infusion time of up to 120 minutes, can be considered to potentially prevent signs and symptoms of hypersensitivity. Monitor patients during infusion and observe patients for at least one hour after infusion is complete for signs and symptoms of hypersensitivity as clinically appropriate. If signs and symptoms of a clinically significant hypersensitivity reaction occur, immediately discontinue administration of VEKLURY and initiate appropriate treatment. (5.1)
- Increased risk of transaminase elevations: Transaminase elevations have been observed in healthy volunteers and have also been reported in patients with COVID-19 who received VEKLURY. Perform hepatic laboratory testing in all patients before starting VEKLURY and while receiving VEKLURY as clinically appropriate. Consider discontinuing VEKLURY if ALT levels increase to greater than 10 times the upper limit of normal. Discontinue VEKLURY if ALT elevation is accompanied by signs or symptoms of liver inflammation. (5.2)
- Risk of reduced antiviral activity when coadministered with chloroquine phosphate or hydroxychloroquine sulfate: Coadministration of VEKLURY and chloroquine phosphate or hydroxychloroquine sulfate is not recommended based on data from cell culture experiments demonstrating a potential antagonistic effect of chloroquine on the intracellular metabolic activation and antiviral activity of VEKLURY. (5.3)

6 ADVERSE REACTIONS

The most common adverse reactions (incidence greater than or equal to 5%, all grades) observed with treatment with VEKLURY are nausea, ALT increased, and AST increased. (6.1)

To report SUSPECTED ADVERSE REACTIONS, contact Gilead Sciences, Inc. at 1-800-GILEAD-5 or FDA at 1-800-FDA-1088 or www.fda.gov/medwatch.

FULL PRESCRIBING INFORMATION

1 INDICATIONS AND USAGE

VEKLURY is indicated for the treatment of coronavirus disease 2019 (COVID-19) in adults and pediatric patients (birth to less than 18 years of age weighing at least 1.5 kg) who are [see Clinical Studies (14)]:

- Hospitalized, or
- Not hospitalized and have mild-to-moderate COVID-19, and are at high risk for progression to severe COVID-19, including hospitalization or death.

2 DOSAGE AND ADMINISTRATION

2.1 Dosage and Administration Overview

- VEKLURY may only be administered in settings in which healthcare providers have immediate access to medications to treat a severe infusion or hypersensitivity reaction, such as anaphylaxis, and the ability to activate the emergency medical system (EMS), as necessary [see Dosage and Administration (2.5), Warnings and Precautions (5.1)].
- Administer VEKLURY for the treatment of COVID-19 in adults and pediatric patients (birth to less than 18 years of age weighing at least 1.5 kg) by intravenous infusion only. Do not administer by any other route.
- VEKLURY for injection must be reconstituted with Sterile Water for Injection prior to diluting with 0.9% sodium chloride injection.

2.2 Testing Before Starting and During Treatment with VEKLURY

Perform hepatic laboratory testing in all patients before starting VEKLURY and while receiving VEKLURY as clinically appropriate [see Warnings and Precautions (5.2) and Use in Specific Populations (8.7)].

Determine prothrombin time in all patients before starting VEKLURY and monitor while receiving VEKLURY as clinically appropriate [see Adverse Reactions (6.1)].

2.3 Recommended Dosage in Adults and Pediatric Patients (Birth to Less than 18 Years of Age Weighing at Least 1.5 kg)

- The recommended dosage for adults and pediatric patients weighing at least 40 kg is a single loading dose of VEKLURY 200 mg on Day 1 via intravenous infusion followed by once-daily maintenance doses of VEKLURY 100 mg from Day 2 via intravenous infusion.
- The recommended dosage for pediatric patients weighing 1.5 kg to less than 40 kg is presented in Table 1.

Table 1 Recommended Dosage in Pediatric Patients Including Term [Gestational age greater than 37 weeks.] Neonates and Infants Weighing 1.5 kg to Less than 40 kg
Pediatric Patient Population | Loading Dose Via Intravenous Infusion | Maintenance Dose Via Intravenous Infusion
Less than 28 days old and at least 1.5 kg | VEKLURY 2.5 mg/kg on Day 1 | VEKLURY 1.25 mg/kg once daily from Day 2
At least 28 days old and 1.5 kg to less than 3 kg | VEKLURY 2.5 mg/kg on Day 1 | VEKLURY 1.25 mg/kg once daily from Day 2
At least 28 days old and 3 kg to less than 40 kg | VEKLURY 5 mg/kg on Day 1 | VEKLURY 2.5 mg/kg once daily from Day 2

The treatment course of VEKLURY should be initiated as soon as possible after diagnosis of symptomatic COVID-19 has been made.

- The recommended total treatment duration for hospitalized patients requiring invasive mechanical ventilation and/or extracorporeal membrane oxygenation (ECMO) is 10 days.
- The recommended treatment duration for hospitalized patients not requiring invasive mechanical ventilation and/or ECMO is 5 days. If a patient does not demonstrate clinical improvement, treatment may be extended for up to 5 additional days for a total treatment duration of up to 10 days.

Non-hospitalized patients:

The treatment course of VEKLURY should be initiated as soon as possible after diagnosis of symptomatic COVID-19 has been made and within 7 days of symptom onset.

- The recommended total treatment duration for non-hospitalized patients diagnosed with mild-to-moderate COVID-19 who are at high risk for progression to severe COVID-19, including hospitalization or death, is 3 days.

VEKLURY must be diluted prior to intravenous infusion. Refer to Dosage and Administration (2.5) for detailed preparation and administration instructions.

2.4 Renal Impairment

No dosage adjustment of VEKLURY is recommended in patients with any degree of renal impairment, including patients on dialysis. VEKLURY may be administered without regard to the timing of dialysis [see Dosage and Administration (2.3) and Use in Specific Populations (8.4, 8.6)].

2.5 Dosage Preparation and Administration

Reconstitution Instructions

Remove the required number of single-dose vial(s) from storage. For each vial:

- Inspect the vial to ensure the container closure is free from defects.
- Aseptically reconstitute VEKLURY lyophilized powder by adding 19 mL of Sterile Water for Injection using a suitably sized syringe and needle per vial, and insert the needle in the center of the vial stopper.
- Only use Sterile Water for Injection to reconstitute VEKLURY lyophilized powder.
- Discard the vial if a vacuum does not pull the Sterile Water for Injection into the vial.
- Immediately shake the vial for 30 seconds.
- Allow the contents of the vial to settle for 2 to 3 minutes. A clear, colorless to yellow solution, free of visible particles, should result.
- If the contents of the vial are not completely dissolved, shake the vial again for 30 seconds and allow the contents to settle for 2 to 3 minutes. Repeat this procedure as necessary until the contents of the vial are completely dissolved. Discard the vial if the contents are not completely dissolved.
- Following reconstitution, each vial contains 100 mg/20 mL (5 mg/mL) of remdesivir solution.
- Use reconstituted product immediately to prepare the diluted drug product. Detailed dilution and administration instruction based on patient’s weight is provided below.

Dilution Instructions for Adults and Pediatric Patients Weighing at Least 40 kg

Care should be taken during admixture to prevent inadvertent microbial contamination. As there is no preservative or bacteriostatic agent present in this product, aseptic technique must be used in preparation of the final parenteral solution. It is always recommended to administer intravenous medication immediately after preparation when possible.

- Reconstituted VEKLURY for injection, containing 100 mg/20 mL remdesivir solution, must be further diluted in either a 100 mL or 250 mL 0.9% sodium chloride injection infusion bag. Refer to Table 2 for instructions.

Table 2 Recommended Dilution Instructions—Reconstituted VEKLURY for Injection in Adults and Pediatric Patients Weighing at Least 40 kg
VEKLURY dose | 0.9% sodium chloride injection infusion bag volume to be used | Volume to be withdrawn and discarded from 0.9% sodium chloride injection infusion bag | Required volume of reconstituted VEKLURY for injection
Loading dose 200 mg (2 vials) | 250 mL | 40 mL | 40 mL (2 × 20 mL)
Loading dose 200 mg (2 vials) | 100 mL | 40 mL | 40 mL (2 × 20 mL)
Maintenance dose 100 mg (1 vial) | 250 mL | 20 mL | 20 mL
Maintenance dose 100 mg (1 vial) | 100 mL | 20 mL | 20 mL

- Withdraw and discard the required volume of 0.9% sodium chloride injection from the bag following instructions in Table 2, using an appropriately sized syringe and needle.
- Inspect the reconstituted VEKLURY for injection vial to ensure the solution is free of particulate matter.
- Withdraw the required volume of reconstituted VEKLURY for injection from the VEKLURY vial following instructions in Table 2, using an appropriately sized syringe. Discard any unused portion remaining in the reconstituted vial.
- Transfer the required volume of reconstituted VEKLURY for injection to the selected infusion bag.
- Gently invert the bag 20 times to mix the solution in the bag. Do not shake.
- The prepared infusion solution can be stored for 24 hours at room temperature (20°C to 25°C [68°F to 77°F]) or 48 hours at refrigerated temperature (2°C to 8°C [36°F to 46°F]) prior to administration.

Administration Instructions for Adults and Pediatric Patients Weighing at Least 40 kg

Do not administer the prepared diluted solution simultaneously with any other medication. The compatibility of VEKLURY injection with intravenous solutions and medications other than 0.9% sodium chloride injection, USP is not known. Administer VEKLURY via intravenous infusion over 30 to 120 minutes.

Administration should be under conditions where management of severe hypersensitivity reactions, such as anaphylaxis, is possible. Monitor patients during infusion and observe patients for at least one hour after infusion is complete for signs and symptoms of hypersensitivity as clinically appropriate [see Warnings and Precautions (5.1)].

Administer the diluted solution with the infusion rate described in Table 3.

Table 3 Recommended Rate of Infusion—Diluted VEKLURY for Injection in Adults and Pediatric Patients Weighing at Least 40 kg
Infusion bag volume | Infusion time | Rate of infusion
250 mL | 30 min | 8.33 mL/min
250 mL | 60 min | 4.17 mL/min
250 mL | 120 min | 2.08 mL/min
100 mL | 30 min | 3.33 mL/min
100 mL | 60 min | 1.67 mL/min
100 mL | 120 min | 0.83 mL/min

Dilution Instructions for Pediatric Patients (Birth to Less than 18 Years of Age) Weighing 1.5 kg to Less than 40 kg

Care should be taken during admixture to prevent inadvertent microbial contamination. As there is no preservative or bacteriostatic agent present in this product, aseptic technique must be used in preparation of the final parenteral solution. It is always recommended to administer intravenous medication immediately after preparation when possible.

- Inspect the reconstituted VEKLURY for injection vial to ensure the reconstituted solution is free of particulate matter.
- For pediatric patients (birth to less than 18 years of age) weighing 1.5 kg to less than 40 kg, the 100 mg/20 mL (5 mg/mL) remdesivir reconstituted solution should be further diluted to a fixed concentration of 1.25 mg/mL using 0.9% sodium chloride injection.
- The final required infusion volume concentration of 1.25 mg/mL remdesivir diluted solution for infusion is based on the pediatric weight-based dosing regimens.
- Small 0.9% sodium chloride injection infusion bags (e.g., 25, 50, or 100 mL) or an appropriately sized syringe should be used for pediatric dosing. The recommended dose is administered via intravenous infusion in a total volume dependent on the dose to yield the target remdesivir concentration of 1.25 mg/mL.
- A syringe and syringe pump may be used for infusion volumes less than 50 mL.

Infusion with IV Bag

- Determine the total infusion volume needed to achieve a final infusion volume concentration of 1.25 mg/mL of remdesivir diluted solution based on the patient's calculated dose.
- Select an appropriately sized infusion bag (either prefilled with 0.9% sodium chloride injection or empty) to prepare VEKLURY diluted solution.
- If using a prefilled 0.9% sodium chloride injection infusion bag, withdraw and discard the amount of diluent equal to the volume of reconstituted VEKLURY solution needed per patient's dose plus a quantity sufficient to achieve a 1.25 mg/mL final volume concentration of remdesivir diluted solution.
- Withdraw the required volume of reconstituted VEKLURY solution into an appropriately sized syringe.
- Transfer the required volume of reconstituted VEKLURY solution to the 0.9% sodium chloride injection infusion bag.
- Gently invert the bag 20 times to mix the solution in the bag. Do not shake.
- If using an empty infusion bag, transfer the required volume of reconstituted VEKLURY solution to the bag, followed by a volume of 0.9% sodium chloride injection sufficient to achieve a 1.25 mg/mL final volume concentration of remdesivir diluted solution.
- The prepared infusion solution is stable for 24 hours at room temperature (20°C to 25°C [68°F to 77°F]) or 48 hours at refrigerated temperature (2°C to 8°C [36°F to 46°F]).

Infusion with Syringe

- Determine the total infusion volume needed to achieve a final infusion volume concentration of 1.25 mg/mL of remdesivir diluted solution based on patient's calculated dose.
- Select an appropriately sized syringe equal to or larger than the calculated total infusion volume of 1.25 mg/mL remdesivir solution needed.
- Withdraw the required volume of reconstituted VEKLURY solution from the vial into the syringe based on patient's calculated dose, followed by the required volume of 0.9% sodium chloride injection needed to achieve a 1.25 mg/mL final volume concentration of remdesivir diluted solution.
- Gently invert the syringe 20 times to mix the solution in the syringe. Do not shake.
- The prepared diluted solution should be used immediately.

Administration Instructions for Pediatric Patients (Birth to Less than 18 Years of Age) Weighing 1.5 kg to Less than 40 kg

The prepared diluted solution should not be administered simultaneously with any other medication. The compatibility of VEKLURY with IV solutions and medications other than 0.9% sodium chloride injection, USP is not known. Administer VEKLURY via intravenous infusion over 30 to 120 minutes. The rate of infusion (mL/min) should be calculated based on the total infusion volume and total infusion time.

Administration should be under conditions where management of severe hypersensitivity reactions, such as anaphylaxis, is possible. Monitor patients during infusion and observe patients for at least one hour after infusion is complete for signs and symptoms of hypersensitivity as clinically appropriate [see Warnings and Precautions (5.1)].

2.6 Storage of Prepared Dosages

After reconstitution, use vials immediately to prepare diluted solution. The diluted VEKLURY solution in the infusion bags can be stored up to 24 hours at room temperature (20°C to 25°C [68°F to 77°F]) prior to administration or 48 hours at refrigerated temperature (2°C to 8°C [36°F to 46°F]).

IMPORTANT:

This product contains no preservative. Any unused portion of a single-dose VEKLURY vial should be discarded after a diluted solution is prepared.

3 DOSAGE FORMS AND STRENGTHS

VEKLURY for injection, 100 mg, available as a sterile, preservative-free white to off-white to yellow lyophilized powder in single-dose vial for reconstitution.

4 CONTRAINDICATIONS

VEKLURY is contraindicated in patients with a history of clinically significant hypersensitivity reactions to VEKLURY or any components of the product [see Warnings and Precautions (5.1)].

5 WARNINGS AND PRECAUTIONS

5.1 Hypersensitivity Including Infusion-related and Anaphylactic Reactions

Hypersensitivity reactions, including infusion-related and anaphylactic reactions, have been observed during and following administration of VEKLURY; most occurred within one hour. Signs and symptoms may include hypotension, hypertension, tachycardia, bradycardia, hypoxia, fever, dyspnea, wheezing, angioedema, rash, nausea, diaphoresis, and shivering. Slower infusion rates, with a maximum infusion time of up to 120 minutes, can be considered to potentially prevent these signs and symptoms. Monitor patients during infusion and observe patients for at least one hour after infusion is complete for signs and symptoms of hypersensitivity as clinically appropriate. If signs and symptoms of a clinically significant hypersensitivity reaction occur, immediately discontinue administration of VEKLURY and initiate appropriate treatment. The use of VEKLURY is contraindicated in patients with known hypersensitivity to VEKLURY or any components of the product [see Contraindications (4)].

5.2 Increased Risk of Transaminase Elevations

Transaminase elevations have been observed in healthy volunteers who received 200 mg of VEKLURY followed by 100 mg doses for up to 10 days; the transaminase elevations were mild (Grade 1) to moderate (Grade 2) in severity and resolved upon discontinuation of VEKLURY. Transaminase elevations have also been reported in patients with COVID-19 who received VEKLURY [see Adverse Reactions (6.1)]. Because transaminase elevations have been reported as a clinical feature of COVID-19, and the incidence was similar in patients receiving placebo versus VEKLURY in clinical trials of VEKLURY, discerning the contribution of VEKLURY to transaminase elevations in patients with COVID-19 can be challenging.

Perform hepatic laboratory testing in all patients before starting VEKLURY and while receiving VEKLURY as clinically appropriate [see Dosage and Administration (2.1) and Use in Specific Populations (8.7)].

- Consider discontinuing VEKLURY if ALT levels increase to greater than 10 times the upper limit of normal.
- Discontinue VEKLURY if ALT elevation is accompanied by signs or symptoms of liver inflammation.

5.3 Risk of Reduced Antiviral Activity When Coadministered with Chloroquine Phosphate or Hydroxychloroquine Sulfate

Coadministration of VEKLURY and chloroquine phosphate or hydroxychloroquine sulfate is not recommended based on data from cell culture experiments demonstrating a potential antagonistic effect of chloroquine on the intracellular metabolic activation and antiviral activity of VEKLURY [see Drug Interactions (7) and Microbiology (12.4)].

6 ADVERSE REACTIONS

The following adverse reactions are discussed in other sections of the labeling:

- Hypersensitivity Including Infusion-related and Anaphylactic Reactions [see Warnings and Precautions (5.1)]
- Increased Risk of Transaminase Elevations [see Warnings and Precautions (5.2)]

6.1 Clinical Trials Experience

Because clinical trials are conducted under widely varying conditions, adverse reaction rates observed in the clinical trials of a drug cannot be directly compared to rates in the clinical trials of another drug and may not reflect the rates observed in practice.

Clinical Trials in Adult Subjects

The safety of VEKLURY is based on data from four Phase 3 studies in 1,476 hospitalized adult subjects with COVID-19, one Phase 3 study in 279 non-hospitalized adult and pediatric subjects (12 years of age and older weighing at least 40 kg) with mild-to-moderate COVID-19, four Phase 1 studies in 131 healthy adults, and from patients with COVID-19 who received VEKLURY under the Emergency Use Authorization or in a compassionate use program.

Clinical Trials Experience in Adults with COVID-19

NIAID ACTT-1 was a randomized, double-blind, placebo-controlled clinical trial in hospitalized subjects with mild, moderate, and severe COVID-19 treated with VEKLURY (n=532) or placebo (n=516) for up to 10 days. Subjects treated with VEKLURY received 200 mg on Day 1 and 100 mg once daily on subsequent days [see Clinical Studies (14.1)]. The collection of adverse event data in this trial was limited to severe (Grade 3) or potentially life-threatening (Grade 4) adverse events, serious adverse events, adverse events leading to study drug discontinuation, and moderate (Grade 2) severity or higher hypersensitivity reactions. Rates of adverse reactions (≥ Grade 3), serious adverse reactions, and adverse reactions leading to treatment discontinuation are presented in Table 4.

Table 4 Summary of Adverse Reaction Rates in Hospitalized Subjects with Mild, Moderate, or Severe COVID-19 in NIAID ACTT-1
Types of Adverse Reactions | VEKLURY N=532 n (%) | Placebo N=516 n (%)
Adverse reactions, Grades ≥3 | 41 (8%) | 46 (9%)
Serious adverse reactions | 2 (0.4%) [Seizure (n=1), infusion-related reaction (n=1).] | 3 (0.6%)
Adverse reactions leading to treatment discontinuation | 11 (2%) [Seizure (n=1), infusion-related reaction (n=1), transaminases increased (n=3), ALT increased and AST increased (n=1), GFR decreased (n=2), acute kidney injury (n=3).] | 15 (3%)

Study GS-US-540-5773 was a randomized, open-label clinical trial in hospitalized subjects with severe COVID-19 treated with VEKLURY 200 mg on Day 1 and 100 mg once daily for 5 (n=200) or 10 days (n=197). Adverse reactions were reported in 33 (17%) subjects in the 5-day group and 40 (20%) subjects in the 10-day group [see Clinical Studies (14.2)]. The most common adverse reactions occurring in at least 5% of subjects in either the VEKLURY 5-day or 10-day group, respectively, were nausea (5% vs 3%), AST increased (3% vs 6%), and ALT increased (2% vs 7%). Rates of any adverse reactions, serious adverse reactions, and adverse reactions leading to treatment discontinuation are presented in Table 5.

Table 5 Summary of Adverse Reaction Rates in Hospitalized Subjects with Severe COVID-19 in Study 5773
Types of Adverse Reactions | VEKLURY 5 Days N=200 n (%) | VEKLURY 10 Days N=197 n (%)
Any adverse reaction, all Grades | 33 (17%) | 40 (20%)
Serious adverse reactions | 3 (2%) [Transaminases increased (n=5), hepatic enzyme increased (n=1), hypertransaminasaemia (n=1).] | 4 (2%)
Adverse reactions leading to treatment discontinuation | 5 (3%) [Transaminases increased (n=4), hepatic enzyme increased (n=2), LFT increased (n=2), hypertransaminasaemia (n=1), ALT increased (n=1), ALT increased and AST increased (n=2), injection site erythema (n=1), rash (n=1).] | 9 (5%)

Study GS-US-540-5774 was a randomized, open-label clinical trial in hospitalized subjects with moderate COVID-19 treated with VEKLURY 200 mg on Day 1 and 100 mg daily for 5 (n=191) or 10 days (n=193), or standard of care (SOC) only (n=200) [see Clinical Studies (14.3)]. Adverse reactions were reported in 36 (19%) subjects in the 5-day group and 25 (13%) subjects in the 10-day group. The most common adverse reaction occurring in at least 5% of subjects in the VEKLURY groups was nausea (7% in the 5-day group, 4% in the 10-day group). Rates of any adverse reactions, serious adverse reactions, and adverse reactions leading to treatment discontinuation are presented in Table 6.

Table 6 Summary of Adverse Reaction [Attribution of events to study drug was not performed for the SOC group.] Rates in Hospitalized Subjects with Moderate COVID-19 in Study 5774
Types of Adverse Reactions | VEKLURY 5 Days N=191 n (%) | VEKLURY 10 Days N=193 n (%)
Any adverse reaction, all Grades | 36 (19%) | 25 (13%)
Serious adverse reactions | 1 (<1%) [Heart rate decreased.] | 0
Adverse reactions leading to treatment discontinuation | 4 (2%) [ALT increased (n=2), ALT increased and AST increased (n=1), hypertransaminasaemia (n=1), blood alkaline phosphatase increased (n=1), rash (n=2), heart rate decreased (n=1).] | 4 (2%)

Study GS-US-540-9012 was a randomized, double-blind, placebo-controlled clinical trial in subjects who were non-hospitalized, were symptomatic for COVID-19 for ≤7 days, had confirmed SARS-CoV-2 infection, and had at least one risk factor for progression to hospitalization treated with VEKLURY (n=279; 276 adults and 3 pediatric subjects 12 years of age and older weighing at least 40 kg) or placebo (n=283; 278 adults and 5 pediatric subjects 12 years of age and older weighing at least 40 kg) for 3 days. Of the 279 subjects treated with VEKLURY, 227 subjects received at least one dose of VEKLURY at an outpatient facility, 44 subjects received at least one dose of VEKLURY in a home healthcare setting, and 8 subjects received at least one dose of VEKLURY at a skilled nursing facility. Subjects treated with VEKLURY received 200 mg on Day 1 and 100 mg once daily on subsequent days [see Clinical Studies (14.4)]. Adverse reactions (all grades) were reported in 34 (12%) subjects in the VEKLURY group and 25 (9%) subjects in the placebo group. The most common adverse reaction occurring in at least 5% of subjects in the VEKLURY group was nausea (6%). There were no serious adverse reactions or adverse reactions leading to treatment discontinuation in either treatment group. Safety in subjects who received VEKLURY in a home healthcare setting was comparable to that observed in the overall GS-US-540-9012 study population, but these findings are based on limited data.

Less Common Adverse Reactions in Adults from Clinical Trials

Clinically significant adverse reactions that were reported in <2% of subjects exposed to VEKLURY in clinical trials are listed below:

- Hypersensitivity reactions [see Warnings and Precautions (5.1)].
- Generalized seizure
- Rash

Laboratory Abnormalities

Study GS-US-399-5505 was a Phase 1, randomized, blinded, placebo-controlled clinical trial in healthy volunteers administered VEKLURY 200 mg on Day 1 and 100 mg for either 4 days or 9 days. Mild (Grade 1, n=8) to moderate (Grade 2, n=1) elevations in ALT were observed in 9 of 20 subjects receiving 10 days of VEKLURY; the elevations in ALT resolved upon discontinuation of VEKLURY. No subjects (0 of 9) who received 5 days of VEKLURY had graded increases in ALT.

The frequencies of laboratory abnormalities (Grades 3–4) occurring in at least 3% of subjects with COVID-19 receiving VEKLURY in Trials NIAID ACTT-1, 5773, and 5774 are presented in Table 7, Table 8, and Table 9, respectively.

Table 7 Laboratory Abnormalities (Grades 3–4) Reported in ≥3% of Hospitalized Subjects with Mild, Moderate, or Severe COVID-19 in NIAID ACTT-1
Laboratory Parameter Abnormality [Frequencies are based on treatment-emergent laboratory abnormalities. Graded per Division of AIDS (DAIDS) Table for Grading the Severity of Adult and Pediatric Adverse Events, Version 2.1 dated July 2017.] | VEKLURY 10 Days N=532 | Placebo N=516
ALT increased | 3% | 6%
AST increased | 6% | 8%
Bilirubin increased | 2% | 5%
Creatinine clearance decreased [Based on the Cockcroft-Gault formula.] | 18% | 20%
Creatinine increased | 15% | 16%
eGFR decreased | 18% | 24%
Glucose increased | 12% | 13%
Hemoglobin decreased | 15% | 22%
Lymphocytes decreased | 11% | 18%
Prothrombin time increased | 9% | 4%

Table 8 Laboratory Abnormalities (Grades 3–4) Reported in ≥3% of Hospitalized Subjects with Severe COVID-19 in Trial 5773
Laboratory Parameter Abnormality [Frequencies are based on treatment-emergent laboratory abnormalities. Graded per Division of AIDS (DAIDS) Table for Grading the Severity of Adult and Pediatric Adverse Events, Version 2.1 dated July 2017.] | VEKLURY 5 Days N=200 | VEKLURY 10 Days N=197
ALT increased | 6% | 8%
AST increased | 7% | 6%
Creatinine clearance decreased [Based on the Cockcroft-Gault formula.] | 10% | 19%
Creatinine increased | 5% | 15%
Glucose increased | 11% | 8%
Hemoglobin decreased | 6% | 8%

Table 9 Laboratory Abnormalities (Grades 3–4) Reported in ≥3% of Hospitalized Subjects with Moderate COVID-19 in Trial 5774
Laboratory Parameter Abnormality [Frequencies are based on treatment-emergent laboratory abnormalities. Graded per Division of AIDS (DAIDS) Table for Grading the Severity of Adult and Pediatric Adverse Events, Version 2.1 dated July 2017.] | VEKLURY 5 Days N=191 | VEKLURY 10 Days N=193 | SOC N=200
ALT increased | 2% | 3% | 8%
Creatinine clearance decreased [Based on the Cockcroft-Gault formula.] | 2% | 5% | 8%
Glucose increased | 4% | 3% | 2%
Hemoglobin decreased | 3% | 1% | 6%
SOC=Standard of care.

The frequencies of laboratory abnormalities (Grades 3–4) occurring in at least 2% of subjects with COVID-19 receiving VEKLURY in Trial GS-US-540-9012 are presented in Table 10.

Table 10 Laboratory Abnormalities (Grades 3–4) Reported in ≥2% of Non-Hospitalized Subjects in Trial 9012
Laboratory Parameter Abnormality [Frequencies are based on treatment-emergent laboratory abnormalities. Graded per Division of AIDS (DAIDS) Table for Grading the Severity of Adult and Pediatric Adverse Events, Version 2.1 dated July 2017.] | VEKLURY 3 Days N=279 | Placebo N=283
Creatinine clearance decreased [Based on the Cockcroft-Gault formula.] | 6% | 2%
Creatinine increased | 3% | 1%
Glucose increased | 6% | 6%
Lymphocytes decreased | 2% | 1%
Prothrombin time increased | 1% | 2%

Clinical Trials Experience in Adults with COVID-19 and Renal Impairment

Study GS-US-540-5912 was a randomized, double-blind, placebo-controlled clinical trial in which 163 hospitalized subjects with confirmed COVID-19 and acute kidney injury (AKI; N=60), chronic kidney disease (CKD; eGFR <30 mL/minute/1.73m^2; N=44), or end-stage renal disease (ESRD; eGFR <15 mL/minute/1.73m^2; N=59) on hemodialysis received VEKLURY for up to 5 days [see Use in Specific Populations (8.6)]. The adverse reactions observed were consistent with those observed in clinical trials of VEKLURY in adults. Adverse reactions (all grades) were reported in 13 (8%) subjects in the VEKLURY group and 3 (4%) subjects in the placebo group. The most common adverse reactions were nausea (1%), abdominal pain (1%), and diarrhea (1%). No subjects experienced serious adverse reactions. One subject permanently discontinued treatment due to an adverse reaction: lipase increased.

The frequencies of laboratory abnormalities (Grades 3–4) occurring in at least 3% of subjects with COVID-19 receiving VEKLURY in Trial GS-US-540-5912 are presented in Table 11.

Table 11 Laboratory Abnormalities (Grades 3–4) Reported in ≥3% of Hospitalized Subjects in Trial 5912
Laboratory Parameter Abnormality [Frequencies are based on treatment-emergent laboratory abnormalities. Graded per Division of AIDS (DAIDS) Table for Grading the Severity of Adult and Pediatric Adverse Events, Version 2.1 dated July 2017.] | VEKLURY 5 Days N=163 | Placebo N=80
Lymphocytes decreased | 27% | 27%
Hemoglobin decreased | 25% | 25%
Glucose increased | 15% | 19%
Uric acid increased | 11% | 4%
Creatinine increased | 12% | 14%
Albumin decreased | 12% | 10%
Lipase increased | 12% | 7%
Prothrombin time increased | 11% | 4%
Prothrombin INR increased | 7% | 4%
AST increased | 6% | 4%
Thromboplastin time increased | 5% | 4%
ALT increased | 5% | 6%
Sodium increased | 3% | 3%
Calcium increased | 3% | 0

Clinical Trials in Pediatric Subjects

Study GS-US-540-5823 was a Phase 2/3, single-arm, open-label clinical trial in hospitalized subjects from birth to <18 years of age and weighing at least 1.5 kg with mild, moderate, and severe COVID-19 treated with weight-based VEKLURY (n=58) for up to 10 days [see Clinical Studies (14.6)]:

- Cohorts 1, 8: Subjects ≥12 years and weighing ≥40 kg (n=12) and subjects <12 years and weighing ≥40 kg (n=5): Received 200 mg on Day 1 and 100 mg once daily on subsequent days.
- Cohorts 2–4: Subjects ≥28 days and weighing ≥20 to <40 kg (n=12); subjects ≥28 days and weighing ≥12 to <20 kg (n=12); and subjects ≥28 days and weighing ≥3 to <12 kg (n=12): Received 5 mg/kg on Day 1 and 2.5 mg/kg once daily on subsequent days.
- Cohort 5: Subjects 14 to <28 days old, gestational age (GA) >37 weeks, and weighing ≥2.5 kg (n=3): Received 5 mg/kg on Day 1 and 2.5 mg/kg once daily on subsequent days.
- Cohorts 6–7: Subjects <14 days old, GA >37 weeks, and weighing ≥2.5 kg at birth (n=1); and subjects <56 days old, GA ≤37 weeks, and weighing ≥1.5 kg at birth (n=1): Received 2.5 mg/kg on Day 1 and 1.25 mg/kg once daily on subsequent days.

The adverse reactions observed were consistent with those observed in clinical trials of VEKLURY in adults.

Infants, children, and adolescents; Cohorts 1–4, 8: Adverse reactions (all grades) were reported in 8 (15%) subjects. The most common adverse reaction occurring in at least 5% of subjects was ALT increased (6%). No subjects experienced serious adverse reactions. Two (4%) subjects permanently discontinued treatment due to adverse reactions (ALT increased [n=1], ALT increased and AST increased and hyperbilirubinemia [n=1]). Laboratory abnormalities (Grades 3–4) occurring in at least 3% of subjects with COVID-19 receiving VEKLURY in Trial 5823 and who had at least one post-baseline value for the specified test were hemoglobin decreased (18%, 9/51), eGFR decreased (18%, 7/40), creatinine increased (10%, 5/52), direct bilirubin increased (9%, 2/23), prothrombin time increased (7%, 3/46), APTT increased (7%, 3/45), lymphocytes decreased (6% 2/33), proteinuria (6%, 2/36), WBC decreased (4%, 2/51), ALT increased (4%, 2/51), glucose increased (4%, 2/52), glycosuria (4%, 2/46), potassium decreased (4%, 2/52).

Neonates and infants; Cohorts 5–7: Laboratory abnormalities (Grades 3–4) were reported in 3/5 subjects: APTT increased (2/5); direct bilirubin increased (1/5); creatinine increased (1/5); prothrombin time increased (1/5); prothrombin/INR increased (1/5); and potassium increased (1/5).

Emergency Use Authorization Experience in Subjects with COVID-19

The following adverse reactions have been identified during use of VEKLURY under Emergency Use Authorization:

- General disorders and administration site conditions: Administration site extravasation
- Skin and subcutaneous tissue disorders: Rash
- Immune system disorders: Anaphylaxis, angioedema, infusion-related reactions, hypersensitivity
- Investigations: Transaminase elevations

7 DRUG INTERACTIONS

7.1 Effects of Other Drugs on VEKLURY

Due to potential antagonism based on data from cell culture experiments, concomitant use of VEKLURY with chloroquine phosphate or hydroxychloroquine sulfate is not recommended [see Warnings and Precautions (5.3) and Microbiology (12.4)].

Based on drug interaction studies conducted with VEKLURY, no clinically significant drug interactions are expected with inducers of cytochrome P450 (CYP) 3A4 or inhibitors of Organic Anion Transporting Polypeptides (OATP) 1B1/1B3 and, P-glycoprotein (P-gp) [see Clinical Pharmacology (12.3)].

7.2 Effects of VEKLURY on Other Drugs

Based on drug interaction studies conducted with VEKLURY, it is a weak inhibitor of CYP3A and does not inhibit OATP1B1/1B3 [see Clinical Pharmacology (12.3)].

8 USE IN SPECIFIC POPULATIONS

8.1 Pregnancy

Risk Summary

Available data from a clinical trial (IMPAACT 2032), published reports, the COVID-PR pregnancy exposure registry, and compassionate use of remdesivir in pregnant individuals have not identified a drug-associated risk of major birth defects, miscarriage, or adverse maternal or fetal outcomes following exposure in the second and third trimester. However, there are insufficient pregnancy data available to evaluate the risk of remdesivir exposure during the first trimester. A study evaluating the pharmacokinetics of remdesivir during pregnancy demonstrated no clinically relevant differences between pregnant and non-pregnant individuals. No dose adjustments are recommended in patients who receive VEKLURY during pregnancy (see Data) and [see Clinical Pharmacology (12.3)]. In nonclinical reproductive toxicity studies, remdesivir demonstrated no adverse effect on embryo-fetal development when administered to pregnant animals at systemic exposures (AUC) of the predominant circulating metabolite of remdesivir (GS-441524) that were 4 times (rats and rabbits) the exposure in humans at the recommended human dose (RHD) (see Data). There are maternal and fetal risks associated with untreated COVID-19 in pregnancy (see Clinical Considerations).

The background risk of major birth defects and miscarriage for the indicated population is unknown. All pregnancies have a background risk of birth defect, loss, or other adverse outcomes. In the U.S. general population, the estimated background risk of major birth defects and miscarriage in clinically recognized pregnancies is 2 to 4% and 15 to 20%, respectively.

Clinical Considerations

Disease-associated maternal and/or embryo-fetal risk

COVID-19 in pregnancy is associated with adverse maternal and fetal outcomes, including preeclampsia, eclampsia, preterm birth, premature rupture of membranes, venous thromboembolic disease, and fetal death.

Data

Human Data

A non-randomized, open-label clinical study (IMPAACT 2032) evaluated pharmacokinetics and safety of up to 10 days of treatment with VEKLURY in 25 hospitalized pregnant and 28 hospitalized non-pregnant individuals of childbearing potential. Subjects received VEKLURY 200 mg once daily for 1 day followed by VEKLURY 100 mg once daily on subsequent days via intravenous infusion. Subjects were enrolled prior to their fourth VEKLURY infusion. Assessments occurred at the following intervals: Screening; Pre-infusion (defined as 48 hours prior to start of first infusion); each infusion day; 48 hours after the last infusion; 7 days after the last infusion; 4 weeks after the last infusion. Assessments also occurred 24 hours post-delivery in subjects who delivered. Treatment with VEKLURY was stopped in subjects who were discharged from the hospital prior to the completion of 10 days of treatment.

Of the 25 pregnant subjects, median age was 33 years (Q1, Q3: 27 years, 37 years); 40% were White, 24% were Black, and 48% were Hispanic or Latino. A total of 9 subjects (36%) were on high-flow oxygen; 12 subjects (48%) were on low-flow oxygen; and 1 subject (4%) was on room air, at baseline. Three subjects (12%) did not have data available on baseline oxygen status. The overall median (Q1, Q3) duration of symptoms prior to hospitalization was 7 (6, 9) days. The overall median (Q1, Q3) duration of symptoms prior to first dose of VEKLURY was 8 (6, 9) days.

Of the 25 pregnant subjects, median gestational age was 28 weeks at baseline (range 22 to 33 weeks) and about half of subjects were in each of the second and third trimester of pregnancy. No clinically relevant differences in the pharmacokinetics of remdesivir or its metabolites (GS-704277 and GS-441524) were observed between pregnant (n=21) and non-pregnant (n=22) individuals [see Clinical Pharmacology (12.3)]. No difference in pharmacokinetics of remdesivir or its metabolites is expected between the first and second/third trimesters. The adverse reactions observed were consistent with those observed in clinical trials of VEKLURY in adults [see Adverse Reactions (6.1)]. There were no adverse reactions in infants born during the study (n=16).

Animal Data

Remdesivir was administered via intravenous injection to pregnant rats and rabbits (up to 20 mg/kg/day) on Gestation Days 6 through 17, and 7 through 20, respectively, and also to rats from Gestation Day 6 to Lactation/Post-partum Day 20. No adverse effects on embryo-fetal (rats and rabbits) or pre/postnatal (rats) development were observed in rats and rabbits at nontoxic doses in pregnant animals. During organogenesis, exposures to the predominant circulating metabolite (GS-441524) were 4 times higher (rats and rabbits) than the exposure in humans at the RHD. In a pre/postnatal development study, exposures to the predominant circulating metabolite of remdesivir (GS-441524) were similar to the human exposures at the RHD.

8.2 Lactation

Risk Summary

A published case report describes the presence of remdesivir and active metabolite GS-441524 in human milk. Available data (n=11) from pharmacovigilance reports do not indicate adverse effects on breastfed infants from exposure to remdesivir and its metabolite through breastmilk. There are no available data on the effects of remdesivir on milk production. In animal studies, remdesivir and metabolites have been detected in the nursing pups of mothers given remdesivir, likely due to the presence of remdesivir in milk (see Data). The developmental and health benefits of breastfeeding should be considered along with the mother's clinical need for VEKLURY and any potential adverse effects on the breastfed child from VEKLURY or from the underlying maternal condition. Breastfeeding individuals with COVID-19 should follow practices according to clinical guidelines to avoid exposing the infant to COVID-19.

Data

Remdesivir and its metabolites were detected in the plasma of nursing rat pups, likely due to the presence of remdesivir and/or its metabolites in milk, following daily intravenous administration of remdesivir to pregnant rats from Gestation Day 6 to Lactation Day 20. Exposures in nursing pups were approximately 1% that of maternal exposure on Lactation Day 10. The concentration of remdesivir in animal milk does not necessarily predict the concentration of drug in human milk.

8.4 Pediatric Use

The safety and effectiveness of VEKLURY for the treatment of COVID-19 have been established in pediatric patients from birth to less than 18 years of age and weighing at least 1.5 kg, who are:

- Hospitalized, or
- Not hospitalized and have mild-to-moderate COVID-19, and are at high risk for progression to severe COVID-19, including hospitalization or death.

Use in this age group is supported by the following:

- Trials in adults [see Clinical Studies (14.1, 14.2, 14.3, 14.4, 14.5)]
- An open-label trial (Study 5823) in 58 hospitalized pediatric subjects [see Adverse Reactions (6.1), Clinical Pharmacology (12.3), and Clinical Studies (14.6)].

Use of VEKLURY in pediatric patients from birth to less than 18 years of age and weighing at least 1.5 kg is supported by Study 5823 where 58 hospitalized pediatric subjects were treated with weight-based VEKLURY for up to 10 days in the following cohorts:

- Cohorts 1–4, 8; infants, children, and adolescents: Subjects ≥12 years and weighing ≥40 kg (n=12); subjects <12 years and weighing ≥40 kg (n=5); subjects ≥28 days and weighing ≥20 to <40 kg (n=12); subjects ≥28 days and weighing ≥12 to <20 kg (n=12); and subjects ≥28 days and weighing ≥3 to <12 kg (n=12);
- Cohorts 5–7; neonates and infants: Subjects 14 to <28 days old, GA >37 weeks, and weighing ≥2.5 kg (n=3); subjects <14 days old, GA >37 weeks, and weighing ≥2.5 kg at birth (n=1); and subjects <56 days old, GA ≤37 weeks, and weighing ≥1.5 kg at birth (n=1).

The safety and pharmacokinetic results in pediatric subjects were similar to those in adults [see Adverse Reactions (6.1), Clinical Pharmacology (12.3), Clinical Studies (14.6)].

Use of VEKLURY in pediatric patients weighing at least 40 kg is further supported by a clinical trial of VEKLURY in non-hospitalized subjects that included 3 pediatric subjects 12 years and older, and by clinical trials in hospitalized subjects that included 30 adult subjects weighing 40 to 50 kg. The safety in this weight group was comparable to adult subjects weighing greater than 50 kg. Thirty-nine pediatric patients 12 years and older and weighing at least 40 kg received VEKLURY in a compassionate use program in hospitalized subjects; the available clinical data from these patients are limited [see Adverse Reactions (6.1) and Clinical Studies (14)].

Use of VEKLURY in pediatric patients with renal impairment is supported by safety data in adults [see Adverse Reactions (6.1), Use in Specific Populations (8.6)]. Limited data are available regarding the safety of VEKLURY in pediatric patients with mild or moderate renal impairment. No data are available regarding the safety of VEKLURY in pediatric patients with severe renal impairment. In adults with severe renal impairment, including those requiring dialysis, exposures of GS-441524 and GS-704277, the metabolites of remdesivir, and betadex sulfobutyl ether sodium (SBECD) are increased [see Clinical Pharmacology (12.3)]. VEKLURY contains SBECD which, when administered intravenously, is eliminated through glomerular filtration and therefore when administered to pediatric patients with renal immaturity or renal impairment, may result in higher exposure to SBECD.

The safety and effectiveness of VEKLURY have not been established in pediatric patients weighing less than 1.5 kg.

8.5 Geriatric Use

Of the 1,062 hospitalized subjects with SARS-CoV-2 infection randomized in ACTT-1, 36% were 65 years or older. Of the 397 hospitalized subjects with SARS-CoV-2 infection randomized in Study GS-US-540-5773, 42% were 65 years or older. Of the 584 hospitalized subjects with SARS-CoV-2 infection randomized in Study GS-US-540-5774, 27% were 65 years or older. Of the 562 non-hospitalized subjects with SARS-CoV-2 infection randomized in Study GS-US-540-9012, 17% were 65 years or older. Reported clinical experience has not identified differences in responses between the elderly and younger patients [see Clinical Studies (14)]. No dosage adjustment is required in patients over the age of 65 years. In general, appropriate caution should be exercised in the administration of VEKLURY and monitoring of elderly patients, reflecting the greater frequency of decreased hepatic, renal, or cardiac function, and of concomitant disease or other drug therapy.

8.6 Renal Impairment

Use of VEKLURY in patients with COVID-19 and renal impairment, including those on dialysis, is supported by safety and pharmacokinetic data from the following:

- a randomized, double-blind, placebo-controlled trial (Study 5912) in adults [see Adverse Reactions (6.1) and Clinical Pharmacology (12.3)].
- an open-label, parallel-group, single-dose trial in subjects with normal renal function and renal impairment (Study 9015) [see Clinical Pharmacology (12.3)].

The pharmacokinetics and safety of VEKLURY in patients with COVID-19 and renal impairment, including those on dialysis, were evaluated in 163 subjects in a randomized, double-blind, placebo-controlled trial, Study GS-US-540-5912 [see Adverse Reactions (6.1) and Clinical Pharmacology (12.3)].

Study GS-US-540-5912 evaluated VEKLURY 200 mg once daily for 1 day followed by VEKLURY 100 mg once daily for 4 days (for a total of up to 5 days of intravenously administered therapy) in 243 hospitalized adult subjects with confirmed COVID-19 and renal impairment. The trial included 90 subjects (37%) with AKI (defined as a 50% increase in serum creatinine within a 48-hour period that was sustained for ≥6 hours despite supportive care), 64 subjects (26%) with CKD (eGFR <30 mL/minute/1.73m^2), and 89 subjects (37%) with ESRD (eGFR <15 mL/minute/1.73m^2) requiring hemodialysis. Subjects were randomized in a 2:1 manner, stratified by ESRD, high-flow oxygen requirement, and region (US vs ex-US) to receive VEKLURY (n=163) or placebo (n=80), plus standard of care.

At baseline, mean age was 69 years (with 62% of subjects aged 65 or older); 57% of subjects were male, 67% were White, 26% were Black, and 3% were Asian. The most common baseline risk factors were hypertension (89%), diabetes mellitus (79%), and cardiovascular or cerebrovascular disease (51%); the distribution of risk factors was similar between the two treatment groups. A total of 45 subjects (19%) were on high-flow oxygen, 144 (59%) were on low-flow oxygen, and 54 (22%) were on room air at baseline; no subjects were on invasive mechanical ventilation (IMV). A total of 182 subjects (75%) were not on renal replacement therapy, and 31 subjects (13%) had received a COVID-19 vaccine.

The safety results in subjects with COVID-19 and renal impairment, including those on dialysis, were consistent with those observed in clinical trials of VEKLURY in adults [see Adverse Reactions (6.1)]. Study GS-US-540-5912 closed prematurely due to feasibility issues and was underpowered to assess for efficacy because of lower than expected enrollment.

The pharmacokinetics and safety of VEKLURY in subjects with normal renal function and renal impairment, including those on dialysis, were evaluated in 75 subjects (43 subjects with renal impairment plus 32 matched control subjects with normal renal function) in an open-label, parallel-group, single-dose trial, Study GS-US-540-9015 [see Clinical Pharmacology (12.3)].

In studies GS-US-540-5912 and GS-US-540-9015, exposures of GS-441524 and GS-704277, the metabolites of remdesivir, and SBECD are increased in subjects with mild to severe renal impairment, including those requiring dialysis, relative to subjects with normal renal function [see Clinical Pharmacology (12.3)].

No dosage adjustment of VEKLURY is recommended for patients with any degree of renal impairment, including those on dialysis [see Dosage and Administration (2.2, 2.4), Use in Specific Populations (8.4)].

8.7 Hepatic Impairment

No dosage adjustment of VEKLURY is recommended for patients with mild, moderate, or severe hepatic impairment (Child-Pugh Class A, B, or C) [see Clinical Pharmacology (12.3)].

Perform hepatic laboratory testing in all patients before starting VEKLURY and while receiving VEKLURY as clinically appropriate [see Dosage and Administration (2.2) and Warnings and Precautions (5.2)].

10 OVERDOSAGE

There is no human experience of acute overdosage with VEKLURY. Treatment of overdose with VEKLURY should consist of general supportive measures including monitoring of vital signs and observation of the clinical status of the patient. There is no specific antidote for overdose with VEKLURY.

11 DESCRIPTION

VEKLURY contains remdesivir, a SARS-CoV-2 nucleotide analog RNA polymerase inhibitor. The chemical name for remdesivir is 2-ethylbutyl N-{(S)-[2-C-(4-aminopyrrolo[2,1-f][1,2,4]triazin-7-yl)-2,5-anhydro-d-altrononitril-6-O-yl]phenoxyphosphoryl}-L-alaninate. It has a molecular formula of C27H35N6O8P and a molecular weight of 602.6 g/mol. Remdesivir has the following structural formula:

VEKLURY for injection contains 100 mg of remdesivir as a sterile, preservative-free lyophilized white to off-white to yellow powder in a single-dose clear glass vial. It requires reconstitution and then further dilution prior to administration by intravenous infusion [see Dosage and Administration (2.5)]. The inactive ingredients are 3 g betadex sulfobutyl ether sodium and may include hydrochloric acid and/or sodium hydroxide for pH adjustment.

12 CLINICAL PHARMACOLOGY

12.1 Mechanism of Action

Remdesivir is an antiviral drug with activity against severe acute respiratory syndrome coronavirus 2 (SARS-CoV-2) [see Microbiology (12.4)].

12.2 Pharmacodynamics

Exposure-Response

Remdesivir and metabolites exposure-response relationships and the time course of pharmacodynamics response are unknown.

Cardiac Electrophysiology

At 3 times the maximum recommended dose, clinically significant QTc interval prolongation was not observed.

12.3 Pharmacokinetics

The pharmacokinetic (PK) properties of remdesivir and metabolites are provided in Table 12. The multiple dose PK parameters of remdesivir and metabolites in adults with COVID-19 are provided in Table 13.

Table 12 Pharmacokinetic Properties of Remdesivir and Metabolites (GS-441524 and GS-704277)
 | Remdesivir | GS-441524 | GS-704277
Absorption
Tmax (h) [Remdesivir administered as a 30-minute IV infusion (Study GS-US-399-5505); range of median observed on Day 1 and Day 5 or 10.] | 0.67–0.68 | 1.51–2.00 | 0.75–0.75
Distribution
% bound to human plasma proteins | 88–93.6 [Range of protein binding for remdesivir from 2 independent experiments show no evidence of concentration-dependent protein binding for remdesivir.] | 2 | 1
Blood-to-plasma ratio | 0.68–1.0 | 1.19 | 0.56
Elimination
t1/2 (h) [Median (Study GS-US-399-4231).] | 1 | 27 | 1.3
Metabolism
Metabolic pathway(s) | CES1 (80%) Cathepsin A (10%) CYP3A (10%) | Not significantly metabolized | HINT1
Excretion
Major route of elimination | Metabolism | Glomerular filtration and active tubular secretion | Metabolism
% of dose excreted in urine [Mean (Study GS-US-399-4231).] | 10 | 49 | 2.9
% of dose excreted in feces | ND | 0.5 | ND
ND=not detected

Table 13 Multiple Dose PK Parameters [Population PK estimates for 30-minute IV infusion of remdesivir for 3 days (Study GS-US-540-9012, n=147).] of Remdesivir and Metabolites (GS-441524 and GS-704277) Following IV Administration of VEKLURY 100 mg to Adults with COVID-19
Parameter Mean [Geometric mean estimates.] (95% CI) | Remdesivir | GS-441524 | GS-704277
Cmax (nanogram per mL) | 2700 (2440, 2990) | 143 (135, 152) | 198 (180, 218)
AUCtau (nanogram∙h per mL) | 1710 (1480, 1980) | 2410 (2250, 2580) | 392 (348, 442)
Ctrough (nanogram per mL) | ND | 61.5 (56.5, 66.8) | ND
CI=Confidence Interval; ND=Not detectable (at 24 hours post-dose)

Specific Populations

Pharmacokinetic differences based on sex, race, age, and renal function on the exposures of remdesivir were evaluated using population pharmacokinetic analysis. Sex and race did not affect the pharmacokinetics of remdesivir and its metabolites (GS-441524 and GS-704277).

Pregnant Individuals

The pharmacokinetics of remdesivir and its circulating metabolites (GS-441524 and GS-704277) were evaluated in pregnant individuals with COVID-19. Exposures (AUCtau, Cmax, and Ctau) of remdesivir and its circulating metabolites during pregnancy were similar to those in non-pregnant individuals (see Table 14).

Table 14 Multiple Dose PK Parameters [Study CO-US-590-5961 (IMPAACT).] of Remdesivir and Metabolites (GS-441524 and GS-704277) Following Intravenous Administration of VEKLURY to Pregnant and Non-Pregnant Individuals with COVID-19
Parameter Mean [Geometric mean estimates.] (90% CI) | Pregnant Individuals (N=21) | Non-Pregnant Individuals (N=22)
Remdesivir
Cmax (nanogram per mL) | 1360 (978, 1890) | 1240 (891, 1720)
AUCtau (nanogram∙h per mL) | 1250 (916, 1700) [N=18] | 1300 (1070, 1590) [N=17]
GS-441524
Cmax (nanogram per mL) | 113 (102, 126) | 121 (108, 136)
AUCtau (nanogram∙h per mL) | 1840 (1630, 2070) [N=20] | 2050 (1780, 2350) [N=21]
Ctau (nanogram per mL) | 51.6 (44.7, 59.6) | 57.1 (48.7, 66.9)
GS-704277
Cmax (nanogram per mL) | 217 (187, 252) | 213 (188, 240)
AUCtau (nanogram∙h per mL) | 454 (406, 508) | 437 (384, 497)
CI=Confidence Interval

Patients with Renal Impairment

The pharmacokinetics of remdesivir and its metabolites (GS-441524 and GS-704277) and excipient SBECD were evaluated in healthy subjects, those with mild (eGFR 60–89 mL/minute/1.73m^2), moderate (eGFR 30–59 mL/minute/1.73m^2), severe (eGFR 15–29 mL/minute/1.73m^2) renal impairment, or kidney failure (eGFR <15 mL/minute/1.73m^2) on dialysis or not on dialysis following a single dose of up to 100 mg of VEKLURY (see Table 15); and in COVID-19 patients with severely reduced kidney function (AKI [defined as a 50% increase in serum creatinine within a 48-hour period that was sustained for ≥6 hours despite supportive care]; CKD [eGFR <30 mL/minute/1.73m^2]; or ESRD [eGFR <15 mL/minute/1.73m^2] requiring hemodialysis) receiving VEKLURY 200 mg loading dose on Day 1 followed by 100 mg from Day 2 to Day 5 (see Table 16). Pharmacokinetic exposures of remdesivir were not affected by renal function or timing of VEKLURY administration around dialysis.

Exposures of GS-441524, GS-704277, and SBECD were up to 7.9-fold, 2.8-fold, and 21-fold higher, respectively, in those with renal impairment compared to those with normal renal function (see Table 15 and Table 16). These changes are not considered to be clinically significant [see Adverse Reactions (6.1) and Use in Specific Populations (8.6)].

Remdesivir was not efficiently removed through hemodialysis. Average hemodialysis clearance of GS-441524 and GS-704277 was 149 mL/minute and 92.6 mL/minute, respectively.

Table 15 Comparison of PK Parameters [Exposures were estimated using noncompartmental analysis from a dedicated Phase 1 renal impairment Study GS-US-540-9015; single doses up to 100 mg were administered; each subject with renal impairment had a matched control participant enrolled with normal renal function (eGFR ≥90 mL/minute/1.73m^2), same sex, and similar BMI (± 20%) and age (± 10 years).] of Remdesivir and Metabolites (GS-441524 and GS-704277) Following IV Administration of Single Dose VEKLURY to Adults with Renal Impairment [eGFR was calculated using Modification of Diet in Renal Disease equation and values represent mL/minute/1.73m^2.] as Compared to Adults with Normal Renal Function
Mean Ratio (90% CI) [No effect=1.0 (0.5–2.0)] | 60–89 mL per minute N=10 | 30–59 mL per minute N=10 | 15–29 mL per minute N=10 | <15 mL per minute
Mean Ratio (90% CI) [No effect=1.0 (0.5–2.0)] | 60–89 mL per minute N=10 | 30–59 mL per minute N=10 | 15–29 mL per minute N=10 | Pre-hemodialysis N=6 | Post-hemodialysis N=6 | No dialysis N=3
Remdesivir
Cmax | 0.96 (0.71, 1.31) | 1.20 (1.01, 1.42) | 0.97 (0.83, 1.13) | 0.89 (0.67, 1.18) | 1.13 (0.79, 1.60) | 0.94 (0.65, 1.35)
AUCinf | 1.00 (0.75, 1.32) | 1.22 (0.98, 1.52) | 0.94 (0.83, 1.07) | 0.80 (0.59, 1.08) | 1.08 (0.72, 1.63) | 0.89 (0.55, 1.43)
GS-441524
Cmax | 1.07 (0.90, 1.26) | 1.44 (1.13, 1.85) | 1.68 (1.28, 2.20) | 2.27 (1.72, 2.99) | 3.07 (2.21, 4.26) | 3.00 (2.63, 3.42)
AUCinf | 1.19 (0.97, 1.47) | 2.02 (1.57, 2.62) | 3.26 (2.39, 4.46) | 4.97 (3.65, 6.77) | 6.22 (4.44, 8.71) | 7.87 (6.49, 9.53)
GS-704277
Cmax | 2.25 (1.20, 4.20) | 1.83 (1.34, 2.49) | 1.27 (0.96, 1.68) | 1.43 (1.00, 2.05) | 1.23 (0.84, 1.80) | 1.76 (1.19, 2.61)
AUCinf | 1.39 (1.13, 1.71) | 2.01 (1.48, 2.73) | 1.78 (1.27, 2.49) | 2.18 (1.61, 2.95) | 2.06 (1.42, 2.97) | 2.81 (1.79, 4.43)
CI=Confidence Interval

Table 16 Comparison of PK Parameters of Remdesivir and Metabolites (GS-441524 and GS-704277) Following IV Administration of VEKLURY (200 mg on Day 1 Followed by 100 mg Daily on Days 2–5) in Adults with COVID-19 with [Population PK estimates for 30-minute IV infusion of remdesivir for 5 days (Study GS-US-540-5912, n=90).] or without [Population PK estimates for 30-minute IV infusion of remdesivir for 3 days (Study GS-US-540-9012, n=148).] Severely Reduced Kidney Function [AKI (defined as a 50% increase in serum creatinine within a 48-hour period that was sustained for ≥6 hours despite supportive care); CKD (eGFR <30 mL/minute/1.73m^2); or ESRD (eGFR <15 mL/minute/1.73m^2) requiring hemodialysis.]
Mean Ratio (90% CI) [No effect=1.0 (0.5–2.0)] | Remdesivir | GS-441524 | GS-704277
Cmax | 1.39 (1.25, 1.54) | 4.98 (4.61, 5.38) | 1.84 (1.63, 2.08)
AUCtau | 1.79 (1.59, 2.01) | 6.59 (6.05, 7.18) | 3.94 (3.50, 4.43)
Ctau | ND | 5.82 (5.25, 6.45) | ND
CI=Confidence Interval; ND=Not detectable (at 24 hours post-dose)

Patients with Hepatic Impairment

The pharmacokinetics of remdesivir and GS-441524 were evaluated in healthy subjects and those with moderate or severe hepatic impairment (Child-Pugh Class B or C) following a single dose of 100 mg of VEKLURY (see Table 17). Relative to subjects with normal hepatic function, mean exposures (AUCinf, Cmax) of remdesivir and GS-441524 were similar in subjects with moderate hepatic impairment and higher in subjects with severe hepatic impairment. The exposure differences in subjects with severe hepatic impairment are not considered to be clinically significant [see Use in Specific Populations (8.7)].

Table 17 Comparison of PK Parameters of Remdesivir and GS-441524 Following IV Administration of Single Dose VEKLURY to Adults with Hepatic Impairment as Compared to Adults with Normal Hepatic Function
Mean Ratio (90% CI) [No effect=1.0 (0.5–2.0)] | Moderate Hepatic Impairment N=10 | Severe Hepatic Impairment N=6
Remdesivir
AUCinf | 1.21 (0.87, 1.67) | 1.56 (1.20, 2.03)
Cmax | 1.10 (0.75, 1.60) | 1.03 (0.70, 1.51)
Unbound AUCinf | 1.15 (0.86, 1.54) | 2.44 (1.93, 3.08)
Unbound Cmax | 1.04 (0.73, 1.48) | 1.57 (1.08, 2.29)
GS-441524
AUCinf | 0.90 (0.69, 1.17) | 1.31 (0.93, 1.84)
Cmax | 1.09 (0.86, 1.38) | 1.48 (1.17, 1.86)
C24 | 0.93 (0.69, 1.24) | 1.16 (0.76, 1.77)
CI=Confidence Interval

Pediatric Patients

Population pharmacokinetic models for remdesivir and its circulating metabolites (GS-441524 and GS-704277), developed using pooled data from studies in healthy subjects and in adult and pediatric patients with COVID-19, were used to estimate pharmacokinetic exposures in pediatric patients aged from birth to <18 years and weighing ≥1.5 kg (Study 5823). Geometric mean estimated exposures (AUCtau, Cmax, and Ctau) for patients ≥28 days to <18 years old and weighing ≥3 kg (Cohorts 1–4 and 8, n=50) at the doses administered were 33% to 130% higher for remdesivir, 3% lower to 60% higher for GS-441524, and 32% to 124% higher for GS-704277 as compared to those in adult patients with COVID-19; however, the increases were not considered clinically significant. Individual estimated exposures (AUCtau, Cmax, and Ctau) for patients 14 to <28 days old, GA >37 weeks, and weighing ≥2.5 kg (Cohort 5, n=3); patients <14 days old, GA >37 weeks, and weighing ≥2.5 kg at birth (Cohort 6, n=1); and patients <56 days old, GA ≤37 weeks, and weighing ≥1.5 kg at birth (Cohort 7, n=1) at the doses administered were higher for remdesivir, GS-441524, and GS-704277 as compared to median exposures in adult patients with COVID-19; however, the increases were not considered clinically significant. As limited PK data were available in Cohorts 5–7, additional analyses were conducted using a simulated population.

Using age and weight distributions from pediatric growth charts, simulated population datasets were created for Cohorts 5–6. Modeling and simulation incorporating maturation functions that account for renal function and drug metabolizing enzyme ontogeny with age were used to predict exposures for subjects <28 days old, GA >37 weeks, and weighing ≥1.5 kg and subjects ≥28 days old and weighing ≥1.5 to <3 kg. Predicted geometric mean exposures (AUCtau, Cmax, and Ctau) at the recommended doses were 10% to 96% higher for remdesivir, 15% lower to 3% higher for GS-441524, and 14% lower to 132% higher for GS-704277 as compared to those in adult patients with COVID-19; however, changes in exposure were not considered clinically significant. Results of simulated population led to the recommended dosing regimen as they more closely align with adult exposures compared to the doses studied.

Plasma exposures of excipient SBECD were generally similar for all pediatric patients at the doses administered in Study GS-US-540-5823 and were similar compared to adults with normal renal function, although data are very limited [see Use in Specific Populations (8.4)].

The multiple dose PK parameters of remdesivir and metabolites in pediatric patients with COVID-19 in Cohorts 1–4 and 8 are provided in Table 18.

Table 18 Multiple Dose PK Parameters [Population PK estimates for 30-minutes IV infusion of remdesivir for up to 10 days (Study GS-US-540-5823).] of Remdesivir and Metabolites (GS-441524 and GS-704277) Following Intravenous Administration of VEKLURY 100 mg (Cohorts 1 and 8) or 2.5 mg/kg (Cohorts 2–4) to Pediatric Patients with COVID-19
 | Cohort 1 | Cohort 8 | Cohort 2 | Cohort 3 | Cohort 4
Parameter Mean [Geometric mean estimates.] (95% CI) | 12 to <18 Years and Weighing ≥40 kg (N=12) | <12 Years and Weighing ≥40 kg (N=5) | 28 Days to <18 Years and Weighing 20 to <40 kg (N=12) | 28 Days to <18 Years and Weighing 12 to <20 kg (N=11) | 28 Days to <18 Years and Weighing 3 to <12 kg (N=10)
Remdesivir
Cmax (nanogram per mL) | 3890 (3110, 4870) | 3920 (2260, 6820) | 5730 (4660, 7050) | 5570 (4250, 7300) | 4870 (3750, 6340)
AUCtau (nanogram∙h per mL) | 2470 (1920, 3160) | 2270 (1200, 4310) | 3510 (2560, 4820) | 3930 (2140, 7210) | 2910 (1880, 4510)
GS-441524
Cmax (nanogram per mL) | 196 (122, 315) | 163 (57.6, 461) | 183 (129, 260) | 171 (130, 223) | 205 (174, 241)
AUCtau (nanogram∙h per mL) | 3430 (1980, 5920) | 2640 (767, 9100) | 2370 (1500, 3740) | 2410 (1740, 3340) | 2850 (2290, 3540)
Ctau (nanogram per mL) | 98.5 (59.1, 164) | 76.2 (23.9, 243) | 59.9 (34.2, 105) | 68.9 (47.4, 100) | 79.7 (59.5, 107)
GS-704277
Cmax (nanogram per mL) | 308 (211, 450) | 266 (137, 514) | 419 (306, 575) | 444 (335, 587) | 385 (294, 504)
AUCtau (nanogram∙h per mL) | 819 (474, 1420) | 518 (192, 1400) | 753 (542, 1050) | 733 (504, 1060) | 687 (484, 973)
CI=Confidence Interval

Drug Interaction Studies

In vitro, remdesivir is a substrate for enzymes CYP3A, carboxylesterase 1 (CES1), and cathepsin A (CatA) and OATP1B1 and P-gp transporters; GS-704277 is a substrate for OATP1B1 and OATP1B3. In vitro, remdesivir is an inhibitor of CYP3A, UGT1A1, OATP1B1, OATP1B3, and MATE1; however, no clinically significant effects on substrates of UGT1A1 or MATE1 are expected. No inhibitory interactions were identified for GS-704277 or GS-441524 in vitro.

Remdesivir is not a substrate for CYP1A1, 1A2, 2B6, 2C9, 2C19, or OATP1B3. GS-704277 and GS-441524 are not substrates for CYP1A1, 1A2, 2B6, 2C8, 2C9, 2D6, or 3A5. GS-441524 is also not a substrate for CYP2C19 or 3A4. GS-704277 and GS-441524 are not substrates for OAT1, OAT3, OCT1, OCT2, MATE1, or MATE2k. GS-441524 is also not a substrate for OATP1B1 or OATP1B3.

Drug-drug interaction studies were conducted with VEKLURY. Table 19 summarizes the pharmacokinetic effects of other drugs on remdesivir and metabolites GS-704277 and GS-441524. Table 20 summarizes the effects of remdesivir on the pharmacokinetics of other drugs.

Table 19 Effect of Other Drugs on Remdesivir and Metabolites GS-704277 and GS-441524
Coadministered Drug | Dose of Coadministered Drug (mg) | Remdesivir Dose (mg) | N | Mean Ratio (90% CI) of Remdesivir, GS-704277, and GS-441524 PK With/Without Coadministered Drug No Effect = 1.00 (0.70–1.43)
Coadministered Drug | Dose of Coadministered Drug (mg) | Remdesivir Dose (mg) | N |  | Cmax | AUCinf | C24
Cyclosporin A [Interaction study conducted in healthy volunteers.] | 400 single dose | 100 single dose | 9 | remdesivir | 1.49 (1.38–1.60) | 1.89 (1.77–2.02) | -
Cyclosporin A [Interaction study conducted in healthy volunteers.] | 400 single dose | 100 single dose | 9 | GS-704277 | 2.51 (2.26–2.78) | 2.97 (2.75–3.20) | -
Cyclosporin A [Interaction study conducted in healthy volunteers.] | 400 single dose | 100 single dose | 9 | GS-441524 | 1.17 (1.12–1.22) | 1.03 (0.99–1.08) | 1.02 (0.95–1.10)
Carbamazepine | 300 twice daily | 100 single dose | 8 | remdesivir | 0.87 (0.78–0.97) | 0.92 (0.83–1.02) | -
Carbamazepine | 300 twice daily | 100 single dose | 8 | GS-704277 | 0.96 (0.84–1.10) | 0.98 (0.92–1.05) | -
Carbamazepine | 300 twice daily | 100 single dose | 8 | GS-441524 | 0.97 (0.88–1.07) | 0.83 (0.78–0.89) | 0.71 (0.64–0.78)
CI=confidence interval

Table 20 Effect of Remdesivir on the Pharmacokinetics of Other Drugs
Coadministered Drug | Dose of Coadministered Drug (mg) | Remdesivir Dose (mg) | N | Mean Ratio (90% CI) of Coadministered Drug PK With/Without Remdesivir No Effect = 1.00 (0.80–1.25)
Coadministered Drug | Dose of Coadministered Drug (mg) | Remdesivir Dose (mg) | N | Cmax | AUCinf
Midazolam [Interaction study conducted in healthy volunteers.] | 2.5 single dose | 200 single dose | 19 | 1.29 (1.19–1.41) | 1.20 (1.14–1.26)
Midazolam | 2.5 single dose | 200 single dose followed by 100 once daily (10 doses) [Midazolam administered with last dose of remdesivir.] | 14 | 1.45 (1.23– 1.70) | 1.30 (1.16– 1.45)
Pitavastatin | 2 single dose | 200 single dose | 20 | 1.05 (0.92–1.20) | 1.17 (1.09–1.24)
CI=confidence Interval

12.4 Microbiology

Mechanism of Action

Remdesivir is an inhibitor of the SARS-CoV-2 RNA-dependent RNA polymerase (RdRp), which is essential for viral replication. Remdesivir is an adenosine nucleotide prodrug that distributes into cells where it is metabolized to a nucleoside monophosphate intermediate by carboxyesterase 1 and/or cathepsin A, depending upon the cell type. The nucleoside monophosphate is subsequently phosphorylated by cellular kinases to form the pharmacologically active nucleoside triphosphate metabolite (GS-443902). Remdesivir triphosphate (RDV-TP) acts as an analog of adenosine triphosphate (ATP) and competes with high selectivity (3.65-fold) over the natural ATP substrate for incorporation into nascent RNA chains by the SARS-CoV-2 RdRp, which results in delayed chain termination (position i+3) during replication of the viral RNA. In a biochemical assay assessing RDV-TP incorporation by the MERS-CoV RdRp complex, RDV-TP inhibited RNA synthesis with an IC50 value of 0.032 µM. RDV-TP can also inhibit viral RNA synthesis following its incorporation into the template viral RNA as a result of read-through by the viral polymerase that may occur at higher nucleotide concentrations. When remdesivir nucleotide is present in the viral RNA template, the efficiency of incorporation of the complementary natural nucleotide is compromised, thereby inhibiting viral RNA synthesis. Remdesivir triphosphate is a weak inhibitor of mammalian DNA and RNA polymerases, including human mitochondrial RNA polymerase.

Antiviral Activity

In Cell Culture

Remdesivir exhibited cell culture antiviral activity against a clinical isolate of SARS‑CoV‑2 in primary human airway epithelial (HAE) cells with a 50% effective concentration (EC50) of 9.9 nM after 48 hours of treatment. Remdesivir inhibited the replication of SARS-CoV-2 in the continuous human lung epithelial cell lines Calu-3 and A549-hACE2 with EC50 values of 280 nM after 72 hours of treatment and 115 nM after 48 hours of treatment, respectively.

Remdesivir EC50 values for SARS-CoV-2 in A549-hACE2 cells were not different when combined with chloroquine phosphate or hydroxychloroquine sulfate at concentrations up to 2.5 µM. In a separate study, the antiviral activity of remdesivir was antagonized by chloroquine phosphate in a dose-dependent manner when the two drugs were co-incubated at clinically relevant concentrations in HEp-2 cells infected with respiratory syncytial virus (RSV). Higher remdesivir EC50 values were observed with increasing concentrations of chloroquine phosphate. Increasing concentrations of chloroquine phosphate or hydroxychloroquine sulfate reduced formation of remdesivir triphosphate in A549-hACE2, HEp-2, and normal human bronchial epithelial cells.

Based on cell culture susceptibility testing by virus yield reduction assay and/or N protein ELISA assay, remdesivir retained similar antiviral activity against clinical isolates of SARS-CoV-2 variants compared to an earlier lineage SARS-CoV-2 (lineage A) isolate, including Alpha (B.1.1.7), Beta (B.1.351), Gamma (P.1), Delta (B.1.617.2), Epsilon (B.1.429), Zeta (P.2), Iota (B.1.526), Kappa (B.1.617.1), Lambda (C.37), and Omicron variants (including B.1.1.529/BA.1, BA.2, BA.2.12.1, BA.2.75, BA.2.86, BA.4, BA.4.6, BA.5, BF.5, BF.7, BQ.1, BQ.1.1, CH.1.1, EG.1.2, EG.5.1, EG.5.1.4, FL.22, HK.3, HV.1, JN.1, XBB, XBB.1.5, XBB.1.5.72, XBB.1.16, XBB.2.3.2, XBC.1.6, and XBF). For these variants, the EC50 fold change values ranged between 0.2 and 2.3 compared to an earlier lineage SARS-CoV-2 (lineage A) isolate. Using the SARS-CoV-2 replicon system, remdesivir retained similar antiviral activity against Omicron subvariants JN.1.7, JN.1.18, KP.2, KP.3, LB.1, and XBB.1.9.2 compared to the wildtype reference replicon (lineage B).

In Clinical Trials

SARS-CoV-2 RNA shedding results from GS-US-540-5776 (ACTT-1) indicate that remdesivir does not significantly reduce the amount of detectable SARS-CoV-2 RNA in oropharyngeal or nasopharyngeal swabs or plasma samples in hospitalized patients compared to placebo, and SARS-CoV-2 RNA shedding results from GS-US-540-9012 indicate that remdesivir does not significantly reduce the amount of detectable SARS-CoV-2 RNA in nasopharyngeal swabs in non-hospitalized patients compared to placebo.

Resistance

In Cell Culture

SARS-CoV-2 isolates with reduced susceptibility to remdesivir have been selected in cell culture. In a selection with GS-441524, the parent nucleoside of remdesivir, virus pools emerged expressing amino acid substitutions at V166A, N198S, S759A, V792I, C799F, and C799R in the viral RdRp (nsp12). When these substitutions were individually introduced into a wild-type recombinant virus by site-directed mutagenesis, 1.7- to 3.5-fold reductions in susceptibility to remdesivir were observed. In a cell culture resistance selection experiment with remdesivir, nsp12 substitution E802D emerged, resulting in a 1.4- to 2.5-fold reduction in susceptibility to remdesivir. In another selection with remdesivir using a SARS-CoV-2 isolate containing the P323L substitution in the viral polymerase, a single amino acid substitution at V166L emerged. Recombinant SARS-CoV-2 with substitutions at P323L alone or P323L+V166L in combination exhibited 1.3- and 1.5-fold reductions in remdesivir susceptibility, respectively.

Cell culture resistance profiling of remdesivir using the rodent CoV murine hepatitis virus identified two substitutions (F476L and V553L) in the viral RdRp (nsp12) at residues conserved across CoVs. Introduction of the corresponding substitutions (F480L and V557L) into SARS-CoV resulted in 6-fold reduction in susceptibility to remdesivir in cell culture and attenuated SARS-CoV pathogenesis in a mouse model. When individually introduced into a SARS-CoV-2 recombinant virus, the corresponding substitutions at F480L and V557L each conferred 2-fold reduced susceptibility to remdesivir.

In Clinical Studies

In a literature publication, the SARS-CoV-2 nsp12 E802D substitution previously identified in a resistance selection experiment emerged in one individual treated with remdesivir. The E802D substitution resulted in a 1.4- to 2.5-fold increase in the remdesivir EC50 value.

In Study CO-US-540-5776 (ACTT-1), among 61 subjects with baseline and post-baseline sequencing data available, the rate of emerging substitutions in the viral RdRp (nsp12) was similar in subjects treated with VEKLURY compared to placebo. Two subjects treated with VEKLURY had an emergent substitution previously identified in resistance selection experiments (nsp12 V792I in one and C799F in the other). These substitutions are associated with 2.2- and 2.5-fold decreases in remdesivir susceptibility, respectively, based on assessments of clinical isolates. In one subject treated with VEKLURY, nsp12 V792F emerged at low frequency and was associated with a 1.8-fold decrease in remdesivir susceptibility.

In Study GS-US-540-5773, among 19 subjects treated with VEKLURY with baseline and post-baseline sequencing data available, the V792F substitution in viral RdRp (nsp12) emerged at low frequency in one subject.

In Study GS-US-540-9012, among 244 subjects with baseline and post-baseline sequencing data available, the rate of emerging substitutions in the viral RdRp (nsp12) was similar in subjects treated with VEKLURY compared to placebo. In one subject treated with VEKLURY, one substitution in the RdRp (nsp12 A376V) emerged and was associated with a 12.6-fold decrease in remdesivir susceptibility in a subgenomic replicon assay. This subject was not hospitalized and showed alleviation of all baseline symptoms, except loss of taste and smell, prior to or on Day 14.

In Study GS-US-540-5912, among 60 subjects with baseline and post-baseline sequencing data available, substitutions in the viral RdRp (nsp12) emerged in 8 subjects treated with VEKLURY. In 4 subjects treated with VEKLURY, three substitutions in the RdRp (nsp12 E136V, M794I, or C799F) emerged and were associated with 2.9-, 2.9-, and 3.4-fold reduced susceptibility to remdesivir in a subgenomic replicon assay.

In Study GS-US-540-5823, among pediatric subjects with baseline and post-baseline sequencing data available, treatment-emergent substitutions in the viral RdRp (nsp12) were observed in 3 of 27 subjects treated with VEKLURY and were evaluated for susceptibility to remdesivir. In one subject, two substitutions (nsp12 substitutions V166L and V792I) emerged and were associated with 1.85- and 3.6-fold decreases in remdesivir susceptibility relative to reference, respectively. This subject was hospitalized at baseline, recovered from COVID-19, and was released from the hospital on Day 13. None of the substitutions observed in any of the other genes (nsp9–10, nsp13–14) encoding for proteins of the viral replication-transcription complex have been associated with reduced susceptibility to remdesivir.

The relationship between the level of reduced susceptibility to remdesivir observed in subgenomic replicon assays and the inhibition of SARS-CoV-2 replication by remdesivir in humans has not been fully established.

13 NONCLINICAL TOXICOLOGY

13.1 Carcinogenesis, Mutagenesis, Impairment of Fertility

Carcinogenesis and Mutagenesis

Given the short-term administration of VEKLURY for the treatment of COVID-19, long-term animal studies to evaluate the carcinogenic potential of remdesivir were not conducted.

Remdesivir was not genotoxic in a battery of assays, including bacterial mutagenicity, chromosome aberration using human peripheral blood lymphocytes, and in vivo rat micronucleus assays.

Impairment of Fertility

Nonclinical toxicity studies in rats demonstrated no adverse effect on male fertility at exposures of the predominant circulating metabolite (GS-441524) approximately 2 times the exposure in humans at the RHD.

Reproductive toxicity, including decreases in corpora lutea, numbers of implantation sites, and viable embryos, was seen when remdesivir was administered by daily intravenous administration at a systemically toxic dose (10 mg/kg) in female rats 14 days prior to mating and during conception; exposures of the predominant circulating metabolite (GS-441524) were 1.3 times the exposure in humans at the RHD.

13.2 Animal Toxicology and/or Pharmacology

Intravenous administration (slow bolus) of remdesivir to male rhesus monkeys at dosage levels of 5, 10, and 20 mg/kg/day for 7 days resulted, at all dose levels, in increased mean urea nitrogen and increased mean creatinine, renal tubular atrophy, and basophilia and casts.

Intravenous administration (slow bolus) of remdesivir to rats at dosage levels of ≥3 mg/kg/day for up to 4 weeks resulted in findings indicative of kidney injury and/or dysfunction.

Kidney-related effects in rats and monkeys were observed at exposures of the predominant circulating metabolite (GS-441524) that are lower than the exposure in humans at the RHD.

14 CLINICAL STUDIES

14.1 Description of Clinical Trials

The efficacy and safety of VEKLURY were evaluated in the trials summarized in Table 21.

Table 21 Trials Conducted with VEKLURY in Subjects with COVID-19
Trial | Population | Trial Arms (N) | Timepoint
NIAID ACTT-1 [Randomized, double-blind, placebo-controlled trial.] (NCT04280705) | Hospitalized with mild/moderate and severe COVID-19 | VEKLURY 10 Days (532) Placebo (516) | 29 Days after Randomization
GS-US-540-5773 [Randomized, open-label trial.] (NCT04292899) | Hospitalized with severe COVID-19 | VEKLURY 5 Days (200) VEKLURY 10 Days (197) | Day 14
GS-US-540-5774 (NCT04292730) | Hospitalized with moderate COVID-19 | VEKLURY 5 Days (191) VEKLURY 10 Days (193) Standard of care (200) | Day 11
GS-US-540-9012 (NCT04501952) | Non-hospitalized with mild-to-moderate COVID-19 and at high risk for progression to severe disease | VEKLURY 3 Days (279) Placebo (283) | Day 28
GS-US-540-5823 (Cohorts 1–8) [Open-label trial, descriptive outcome analyses.] (NCT04431453) | Hospitalized pediatric subjects from birth to <18 years of age and weighing at least 1.5 kg with COVID-19 | VEKLURY up to 10 Days (58) | Day 10
COVID-19: coronavirus disease 2019

14.2 NIAID ACTT-1 Study in Hospitalized Subjects with Mild/Moderate and Severe COVID-19

A randomized, double-blind, placebo-controlled clinical trial (ACTT-1) of hospitalized adult subjects with confirmed SARS-CoV-2 infection and mild, moderate, or severe COVID-19 compared treatment with VEKLURY for 10 days (n=541) with placebo (n=521). Mild/moderate disease was defined as SpO2 >94% and respiratory rate <24 breaths/minute without supplemental oxygen; severe disease was defined as an SpO2 ≤94% on room air, a respiratory rate ≥24 breaths/minute, an oxygen requirement, or a requirement for mechanical ventilation. Subjects had to have at least one of the following to be enrolled in the trial: radiographic infiltrates by imaging, SpO2 ≤94% on room air, a requirement for supplemental oxygen, or a requirement for mechanical ventilation. Subjects treated with VEKLURY received 200 mg on Day 1 and 100 mg once daily on subsequent days, for 10 days of treatment via intravenous infusion. Treatment with VEKLURY was stopped in subjects who were discharged from the hospital prior to the completion of 10 days of treatment.

At baseline, mean age was 59 years (with 36% of subjects aged 65 or older); 64% of subjects were male, 53% were White, 21% were Black, and 13% were Asian; 24% were Hispanic or Latino; 105 subjects had mild/moderate disease (10% in both treatment groups); 957 subjects had severe disease (90% in both treatment groups). Subjects in this trial were unvaccinated. A total of 285 subjects (27%) (n=131 received VEKLURY) were on invasive mechanical ventilation or ECMO. The most common comorbidities were hypertension (51%), obesity (45%), and type 2 diabetes mellitus (31%); the distribution of comorbidities was similar between the two treatment groups.

The primary clinical endpoint was time to recovery within 29 days after randomization. Recovery was defined as discharged from the hospital without limitations on activities, discharged from the hospital with limitations on activities and/or requiring home oxygen, or hospitalized but not requiring supplemental oxygen and no longer requiring ongoing medical care. The median time to recovery was 10 days in the VEKLURY group compared to 15 days in the placebo group (recovery rate ratio 1.29 [95% CI 1.12 to 1.49], p<0.001). Among subjects with mild/moderate disease at enrollment (n=105), the median time to recovery was 5 days in both the VEKLURY and placebo groups (recovery rate ratio 1.22 [95% CI 0.82 to 1.81]). Among subjects with severe disease at enrollment (n=957), the median time to recovery was 11 days in the VEKLURY group compared to 18 days in the placebo group (recovery rate ratio 1.31 [95% CI 1.12 to 1.52]).

A key secondary endpoint was clinical status on Day 15 assessed on an 8-point ordinal scale consisting of the following categories:

1. not hospitalized, no limitations on activities;
2. not hospitalized, limitation on activities and/or requiring home oxygen;
3. hospitalized, not requiring supplemental oxygen - no longer requires ongoing medical care;
4. hospitalized, not requiring supplemental oxygen - requiring ongoing medical care (COVID-19 related or otherwise);
5. hospitalized, requiring supplemental oxygen;
6. hospitalized, on noninvasive ventilation or high-flow oxygen devices;
7. hospitalized, on invasive mechanical ventilation or ECMO; and
8. death.

Overall, the odds of improvement in the ordinal scale were higher in the VEKLURY group at Day 15 when compared to the placebo group (odds ratio 1.54 [95% CI 1.25 to 1.91]).

Overall, 29-day mortality was 11% for the VEKLURY group vs 15% for the placebo group (hazard ratio 0.73 [95% CI 0.52 to 1.03]).

14.3 Study GS-US-540-5773 in Hospitalized Subjects with Severe COVID-19

A randomized, open-label multi-center clinical trial (Study 5773) in adult subjects with confirmed SARS-CoV-2 infection, an SpO2 of ≤94% on room air, and radiological evidence of pneumonia compared 200 subjects who received VEKLURY for 5 days with 197 subjects who received VEKLURY for 10 days. Treatment with VEKLURY was stopped in subjects who were discharged from the hospital prior to completion of their protocol-defined duration of treatment. Subjects on mechanical ventilation at screening were excluded. All subjects received 200 mg of VEKLURY on Day 1 and 100 mg once daily on subsequent days via intravenous infusion, plus standard of care.

At baseline, the median age of subjects was 61 years (range, 20 to 98 years); 64% were male, 75% were White, 12% were Black, and 12% were Asian; 22% were Hispanic or Latino. More subjects in the 10-day group than the 5-day group required invasive mechanical ventilation or ECMO (5% vs 2%), or high-flow oxygen support (30% vs 25%), at baseline. Subjects in this trial were unvaccinated. Median duration of symptoms and hospitalization prior to first dose of VEKLURY were similar across treatment groups.

The primary endpoint was clinical status on Day 14 assessed on a 7-point ordinal scale consisting of the following categories:

1. death;
2. hospitalized, receiving invasive mechanical ventilation or ECMO;
3. hospitalized, receiving noninvasive ventilation or high-flow oxygen devices;
4. hospitalized, requiring low-flow supplemental oxygen;
5. hospitalized, not requiring supplemental oxygen but receiving ongoing medical care (related or not related to COVID-19);
6. hospitalized, requiring neither supplemental oxygen nor ongoing medical care (other than that specified in the protocol for remdesivir administration); and
7. not hospitalized.

Overall, after adjusting for between-group differences at baseline, subjects receiving a 5-day course of VEKLURY had similar clinical status at Day 14 as those receiving a 10-day course (odds ratio for improvement 0.75 [95% CI 0.51 to 1.12]). There were no statistically significant differences in recovery rates or mortality rates in the 5-day and 10-day groups once adjusted for between-group differences at baseline. All-cause mortality at Day 28 was 12% vs 14% in the 5- and 10-day treatment groups, respectively.

14.4 Study GS-US-540-5774 in Hospitalized Subjects with Moderate COVID-19

A randomized, open-label multi-center clinical trial (Study 5774) of hospitalized adult subjects with confirmed SARS-CoV-2 infection, SpO2 >94% and radiological evidence of pneumonia compared treatment with VEKLURY for 5 days (n=191) and treatment with VEKLURY for 10 days (n=193) with standard of care (n=200). Treatment with VEKLURY was stopped in subjects who were discharged from the hospital prior to completion of their protocol-defined duration of treatment. Subjects treated with VEKLURY received 200 mg on Day 1 and 100 mg once daily on subsequent days via intravenous infusion.

At baseline, the median age of subjects was 57 years (range, 12 to 95 years); 61% were male, 61% were White, 19% were Black, and 19% were Asian; 18% were Hispanic or Latino. Subjects in this trial were unvaccinated. Baseline clinical status, oxygen support status, and median duration of symptoms and hospitalization prior to first dose of VEKLURY were similar across treatment groups.

The primary endpoint was clinical status on Day 11 assessed on a 7-point ordinal scale consisting of the following categories:

1. death;
2. hospitalized, receiving invasive mechanical ventilation or ECMO;
3. hospitalized, receiving noninvasive ventilation or high-flow oxygen devices;
4. hospitalized, requiring low-flow supplemental oxygen;
5. hospitalized, not requiring supplemental oxygen but receiving ongoing medical care (related or not related to COVID-19);
6. hospitalized, requiring neither supplemental oxygen nor ongoing medical care (other than that specified in the protocol for remdesivir administration); and
7. not hospitalized.

Overall, the odds of improvement in the ordinal scale were higher in the 5-day VEKLURY group at Day 11 when compared to those receiving only standard of care (odds ratio 1.65 [95% CI 1.09 to 2.48], p=0.017). The odds of improvement in clinical status with the 10-day treatment group when compared to those receiving only standard of care were not statistically significant (odds ratio 1.31 [95% CI 0.88 to 1.95]). All-cause mortality at Day 28 was ≤2% in all treatment groups.

14.5 Study GS-US-540-9012 in Non-Hospitalized Subjects with Mild-to-Moderate COVID-19 and at High Risk for Progression to Severe Disease

A randomized, double-blind, placebo-controlled, clinical trial (Study 9012) evaluated VEKLURY 200 mg once daily for 1 day followed by VEKLURY 100 mg once daily for 2 days (for a total of 3 days of intravenously administered therapy) in 554 adult and 8 pediatric subjects (12 years of age and older and weighing at least 40 kg) who were non-hospitalized, had mild-to-moderate COVID-19, were symptomatic for COVID-19 for ≤7 days, had confirmed SARS-CoV-2 infection, and had at least one risk factor for progression to hospitalization. Risk factors for progression to hospitalization included age ≥60 years, obesity (BMI ≥30), chronic lung disease, hypertension, cardiovascular or cerebrovascular disease, diabetes mellitus, immunocompromised state, chronic mild or moderate kidney disease, chronic liver disease, current cancer, and sickle cell disease. Subjects who received, required, or were expected to require supplemental oxygen were excluded from the trial. Subjects were randomized in a 1:1 manner, stratified by residence in a skilled nursing facility (yes/no), age (<60 vs ≥60 years), and region (US vs ex-US) to receive VEKLURY (n=279) or placebo (n=283), plus standard of care.

At baseline, mean age was 50 years (with 30% of subjects aged 60 or older); 52% were male, 80% were White, 8% were Black, and 2% were Asian; 44% were Hispanic or Latino; median body mass index was 30.7 kg/m^2. Subjects in this trial were unvaccinated. VEKLURY or placebo was first administered to subjects in outpatient facilities (84%), home healthcare settings (13%), or skilled nursing facilities (3%). The most common comorbidities were diabetes mellitus (62%), obesity (56%), and hypertension (48%). Median (Q1, Q3) duration of symptoms prior to treatment was 5 (3, 6) days; median viral load was 6.3 log10 copies/mL at baseline. The baseline demographics and disease characteristics were well balanced across the VEKLURY and placebo treatment groups.

The primary endpoint was the proportion of subjects with COVID-19 related hospitalization (defined as at least 24 hours of acute care) or all-cause mortality through Day 28. Events occurred in 2 (0.7%) subjects treated with VEKLURY compared to 15 (5.3%) subjects concurrently randomized to placebo (hazard ratio 0.134 [95% CI 0.031 to 0.586]; p=0.0076). No deaths were observed through Day 28.

14.6 Study GS-US-540-5823 in Hospitalized Pediatric Subjects with COVID-19

The primary objectives of this Phase 2/3 single-arm, open-label clinical trial (Study GS-US-540-5823) were to evaluate pharmacokinetics and safety of up to 10 days of treatment with VEKLURY in pediatric subjects. A total of 58 pediatric subjects from birth (including preterm to term infants) to <18 years of age and weighing at least 1.5 kg with confirmed SARS-CoV-2 infection and mild, moderate, or severe COVID-19 was evaluated in eight cohorts:

- Cohorts 1–4, 8; infants, children, and adolescents: Subjects ≥12 years and weighing ≥40 kg (n=12); subjects <12 years and weighing ≥40 kg (n=5); subjects ≥28 days and weighing ≥20 to <40 kg (n=12); subjects ≥28 days and weighing ≥12 to <20 kg (n=12); and subjects ≥28 days and weighing ≥3 to <12 kg (n=12). Subjects weighing ≥40 kg received 200 mg of VEKLURY on Day 1 followed by VEKLURY 100 mg once daily on subsequent days; subjects weighing ≥3 kg to <40 kg received VEKLURY 5 mg/kg on Day 1 followed by VEKLURY 2.5 mg/kg once daily on subsequent days;
- Cohorts 5–7; neonates and infants: Subjects 14 to <28 days old, GA >37 weeks, and weighing ≥2.5 kg (n=3); subjects <14 days old, GA >37 weeks, and weighing ≥2.5 kg at birth (n=1); and subjects <56 days old, GA ≤37 weeks, and weighing ≥1.5 kg at birth (n=1). Subjects 14 to <28 days old, GA >37 weeks, and weighing ≥2.5 kg received VEKLURY 5 mg/kg on Day 1 followed by VEKLURY 2.5 mg/kg once daily on subsequent days. Subjects <14 days old, GA >37 weeks, and weighing at least 2.5 kg at birth, and subjects <56 days old, GA ≤37 weeks, and weighing ≥1.5 kg at birth, received VEKLURY 2.5 mg/kg on Day 1 followed by VEKLURY 1.25 mg/kg once daily on subsequent days.

Assessments occurred at the following intervals: Screening; Day 1 (Baseline); Days 2–10, or until discharge, whichever came earlier; Follow-Up on Day 30 (±5). Treatment with VEKLURY was stopped in subjects who were discharged from the hospital prior to the completion of 10 days of treatment.

Infants, children, and adolescents: At baseline, median age was 7 years (Q1, Q3: 2 years, 12 years); 57% were female, 70% were White, 30% were Black, and 44% were Hispanic or Latino; median weight was 25 kg (range: 4 to 192 kg). Subjects in this trial were unvaccinated. A total of 12 subjects (23%) were on invasive mechanical ventilation, 18 (34%) were on non-invasive ventilation or high-flow oxygen; 10 (19%) were on low-flow oxygen; and 13 (25%) were on room air, at baseline. The overall median (Q1, Q3) duration of symptoms and hospitalization prior to first dose of VEKLURY was 5 (3, 7) days and 1 (1, 3) day, respectively.

The descriptive outcome analyses showed treatment with VEKLURY for up to 10 days resulted in an overall median (Q1, Q3) change from baseline in clinical status (assessed on a 7-point ordinal scale ranging from death [score of 1] to ventilatory support and decreasing levels of oxygen to hospital discharge [score of 7]) of +2.0 (1.0, 4.0) points on Day 10.

Recovery (defined as an improvement from a baseline clinical status score of 2 through 5 to a score of 6 or 7, or an improvement from a baseline score of 6 to a score of 7) was reported for 62% of subjects on Day 10; median (Q1, Q3) time to recovery was 7 (5, 16) days.

Overall, 60% of subjects were discharged by Day 10, and 83% of subjects were discharged by Day 30. Three subjects (6%) from Cohorts 1–4 and Cohort 8 died during the study.

Neonates and infants: At baseline, subjects ranged in age from 12 to 30 days; 3/5 were female, 4/5 were White, 1/5 was Black; weight ranged from 2.2 to 3.5 kg. Three subjects were on invasive mechanical ventilation and 2 were on high-flow oxygen. The duration of symptoms and hospitalization prior to first dose of VEKLURY ranged from 2 to 9 days and 1 to 9 days, respectively.

The descriptive outcome analyses showed treatment with VEKLURY for up to 10 days resulted in recovery (defined as an improvement from a baseline clinical status score of 2 through 5 to a score of 6 or 7, or an improvement from a baseline score of 6 to a score of 7) for 3 subjects, including for one subject by Day 10. Time to recovery ranged from 9 to 19 days.

Overall, a total of 3 subjects were discharged by Day 30, of which one subject was discharged by Day 10. No subjects from Cohorts 5–7 died during the study.

16 HOW SUPPLIED/STORAGE AND HANDLING

How Supplied

VEKLURY for injection, 100 mg (NDC 61958-2901-2) is supplied as a single-dose vial containing a sterile, preservative-free white to off-white to yellow lyophilized powder. It requires reconstitution and further dilution prior to administration by intravenous infusion [see Dosage and Administration (2.5)]. Discard unused portion. The container closure is not made with natural rubber latex.

Storage and Handling

These products contain no preservative; therefore, partially used vials should be discarded [see Dosage and Administration (2.6)].

Store VEKLURY for injection, 100 mg vials below 30°C (below 86°F) until required for use.

After reconstitution, use vials immediately to prepare diluted solution. Dilute the reconstituted solution in 0.9% sodium chloride injection, USP within the same day as administration. The diluted VEKLURY solution in the infusion bags can be stored up to 24 hours at room temperature (20°C to 25°C [68°F to 77°F]) prior to administration or 48 hours at refrigerated temperature (2°C to 8°C [36°F to 46°F]).

17 PATIENT COUNSELING INFORMATION

Advise the patient to read the FDA-approved patient labeling (Patient Information).

Hypersensitivity Reactions

Inform patients that hypersensitivity reactions have been seen in patients receiving VEKLURY during and after infusion. Advise patients to inform their healthcare provider if they experience any of the following: changes in heart rate; fever; shortness of breath, wheezing; swelling of the lips, face, or throat; rash; nausea; sweating; or shivering [see Warnings and Precautions (5.1)].

Increased Risk of Transaminase Elevations

Inform patients that VEKLURY may increase the risk of hepatic laboratory abnormalities. Advise patients to alert their healthcare provider immediately if they experience any symptoms of liver inflammation [see Warnings and Precaution (5.2)].

Drug Interactions

Inform patients that VEKLURY may interact with other drugs. Advise patients to report to their healthcare provider the use of any other prescription or nonprescription medication or herbal products, including chloroquine phosphate or hydroxychloroquine sulfate [see Warnings and Precautions (5.3), Drug Interactions (7), and Microbiology (12.4)].

Pregnancy

Inform patients to notify their healthcare provider in the event of a pregnancy [see Use in Specific Populations (8.1)].

VEKLURY is a trademark of Gilead Sciences, Inc., or its related companies. All other trademarks referenced herein are the property of their respective owners.

© 2025 Gilead Sciences, Inc. All rights reserved

PATIENT INFORMATION

VEKLURY® (VEK-lur-ee)
(remdesivir)
for injection

What is VEKLURY?
VEKLURY is a prescription medicine used for the treatment of coronavirus disease 2019 (COVID-19) in adults and children weighing at least 3 pounds (1.5 kg) who are:

- Hospitalized, or
- Not hospitalized and have mild-to-moderate COVID-19, and are at high risk for progression to severe COVID-19, including hospitalization or death.

It is not known if VEKLURY is safe and effective in children weighing less than 3 pounds (1.5 kg).

Do not take VEKLURY if you are allergic to remdesivir or any of the ingredients in VEKLURY. See the end of this leaflet for a complete list of ingredients in VEKLURY.

Before receiving VEKLURY, tell your healthcare provider about all of your medical conditions, including if you:

- have liver problems
- are pregnant or plan to become pregnant. It is not known if VEKLURY may harm your unborn baby if taken during the first trimester of pregnancy. Tell your healthcare provider right away if you are or if you become pregnant.
- are breastfeeding or plan to breastfeed. VEKLURY can pass into your breast milk. Talk to your healthcare provider about the best way to feed your baby.

Tell your healthcare provider about all the medicines you take, including prescription and over-the-counter medicines, vitamins, and herbal supplements. VEKLURY may interact with other medicines.
Especially tell your healthcare provider if you are taking the medicines chloroquine phosphate or hydroxychloroquine sulfate.

How will I receive VEKLURY?

- Hospitalized: VEKLURY is given to you through a vein by intravenous (IV) infusion one time each day for up to 10 days. Your healthcare provider will decide how many doses you need.
- Not hospitalized: VEKLURY is given to you through a vein by intravenous (IV) infusion one time each day for 3 days.
- Your healthcare provider will do certain blood tests before starting and during treatment with VEKLURY.

What are the possible side effects of VEKLURY?
VEKLURY may cause serious side effects, including:

- Allergic reactions. Allergic reactions can happen during or after infusion with VEKLURY. Your healthcare provider will monitor you for signs and symptoms of allergic reactions during your infusion and for at least 1 hour after your infusion. Tell your healthcare provider right away if you get any of the following signs and symptoms of an allergic reaction:

- changes in your heart rate
- fever
- shortness of breath, wheezing
- swelling of the lips, face, or throat

- rash
- nausea
- sweating
- shivering

- Increase in liver enzymes. Increases in liver enzymes are common in people who have received VEKLURY and may be a sign of liver injury. Your healthcare provider will do blood tests to check your liver enzymes before and during treatment with VEKLURY as needed. Your healthcare provider may stop treatment with VEKLURY if you develop liver problems.

The most common side effect of VEKLURY is nausea.
These are not all of the possible side effects of VEKLURY.
Call your doctor for medical advice about side effects. You may report side effects to FDA at 1-800-FDA-1088.

General information about the safe and effective use of VEKLURY.
Medicines are sometimes prescribed for purposes other than those listed in a Patient Information leaflet. You can ask your pharmacist or healthcare provider for information about VEKLURY that is written for healthcare professionals.

What are the ingredients in VEKLURY?
Active ingredient: remdesivir
Inactive ingredients: betadex sulfobutyl ether sodium and may include hydrochloric acid and/or sodium hydroxide for pH adjustment.
Manufactured and distributed by: Gilead Sciences, Inc., Foster City, CA 94404
VEKLURY is a trademark of Gilead Sciences, Inc., or its related companies. All other trademarks referenced herein are the property of their respective owners.
© 2025 Gilead Sciences, Inc. All rights reserved.
214787-GS-022
For more information, call 1-800-445-3235 or go to www.VEKLURY.com.

This Patient Information has been approved by the U.S. Food and Drug Administration.

Revised: 10/2025

PRINCIPAL DISPLAY PANEL - 100 mg Vial Label

Veklury®
(remdesivir) for injection
100 mg/vial

Single-Dose Vial: Discard
Unused Portion

Must be reconstituted and
further diluted prior to use.
For Intravenous Infusion.

90288101
Rx only

PRINCIPAL DISPLAY PANEL - 100 mg Vial Carton

NDC 61958-2901-2
Rx only

Veklury®
(remdesivir) for injection
100 mg/vial

Single-Dose Vial: Discard
Unused Portion

Must be reconstituted and
further diluted prior to use.
For Intravenous Infusion.

GILEAD